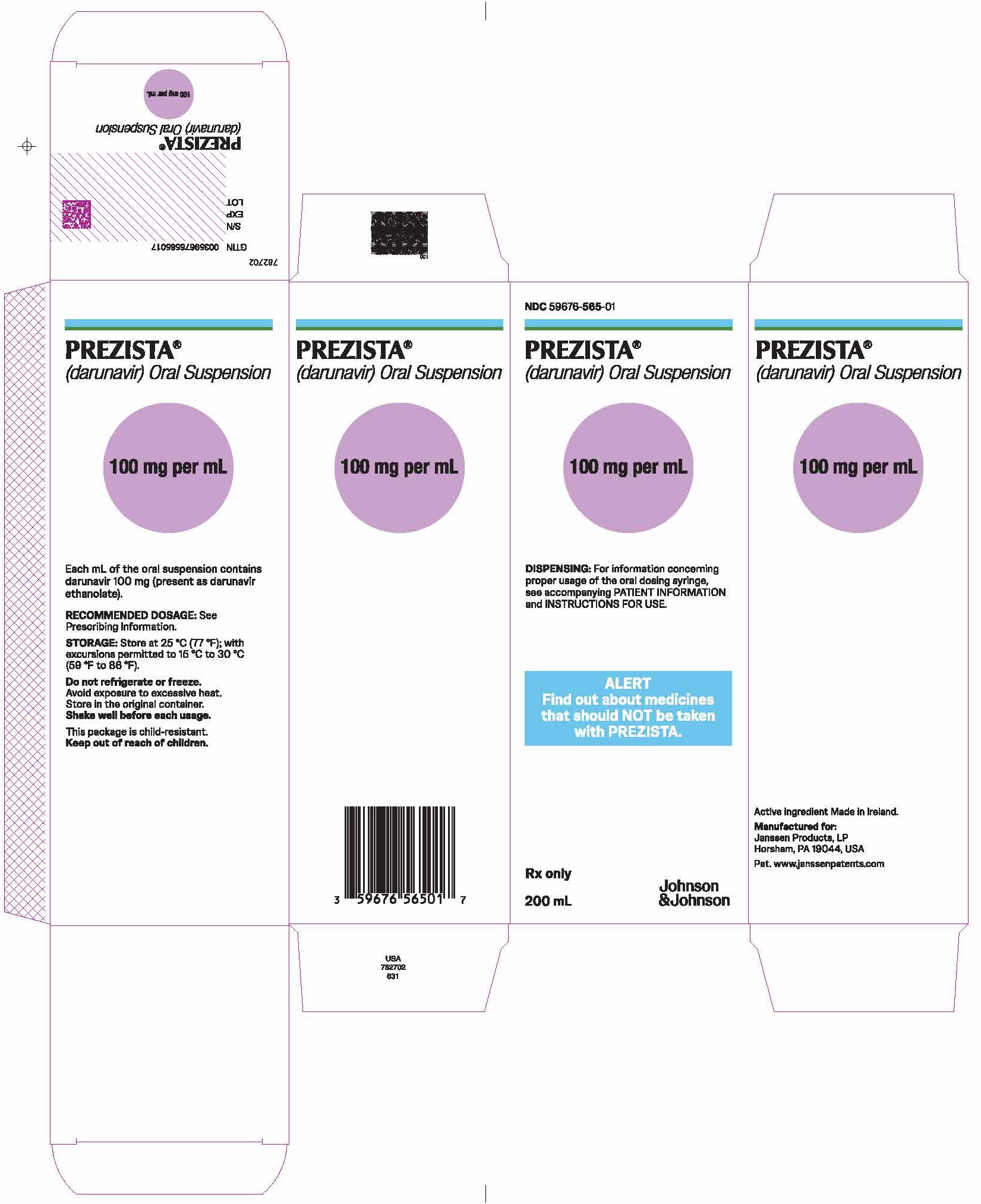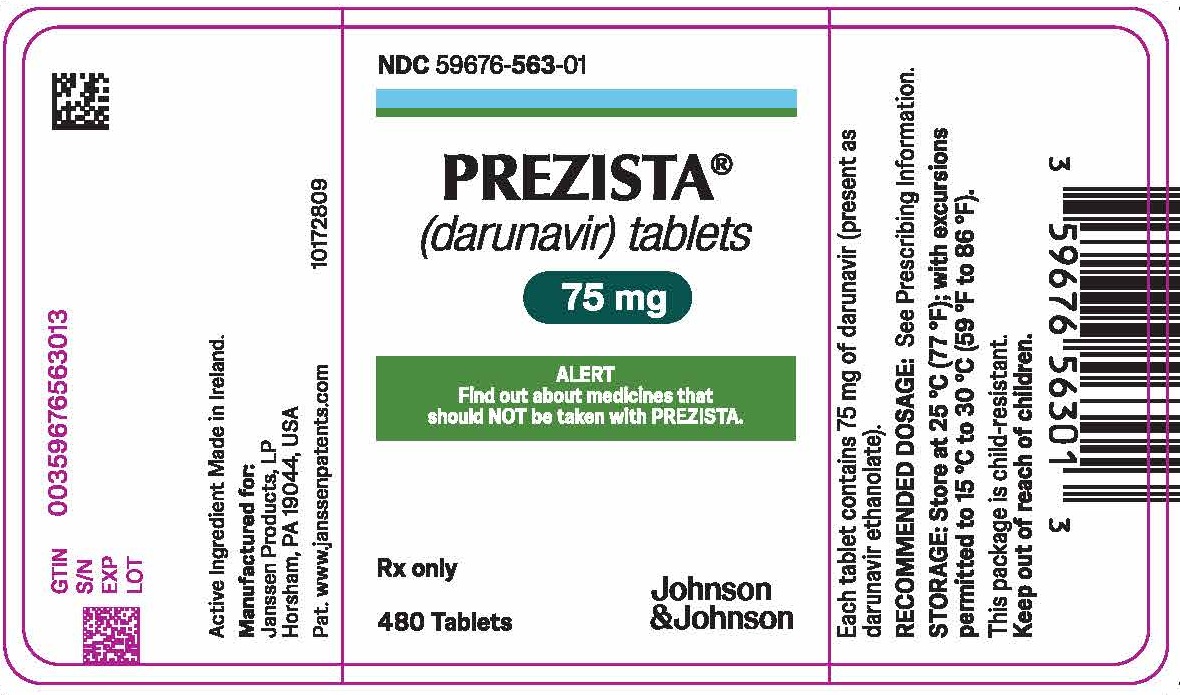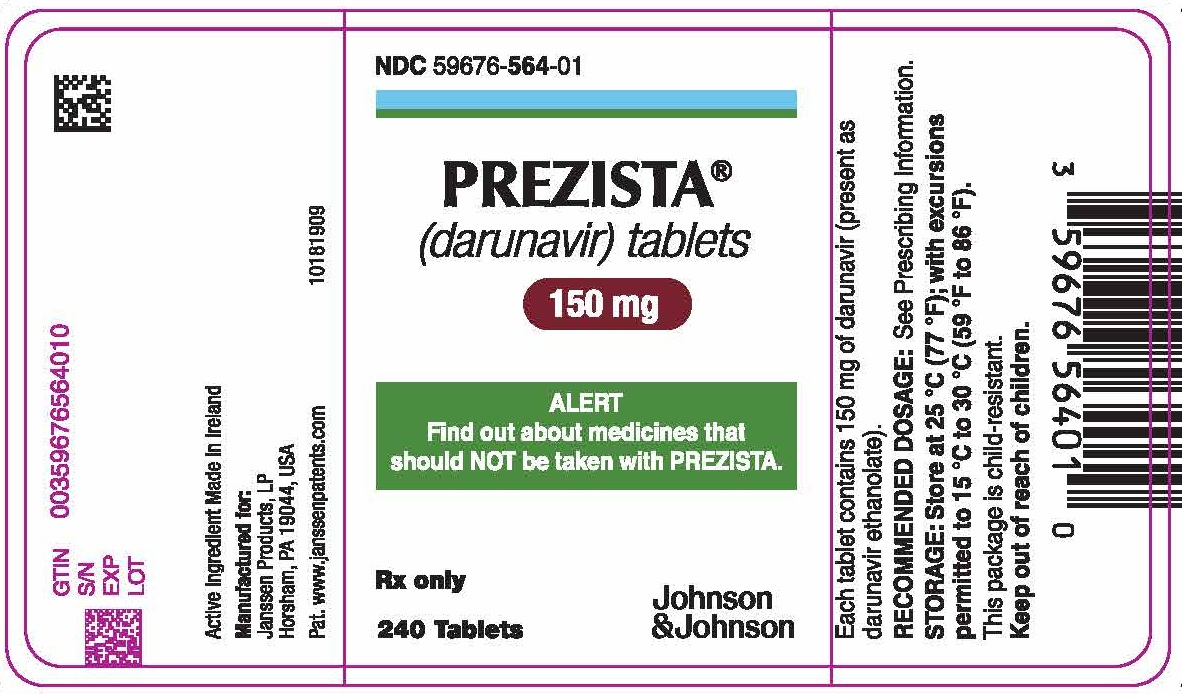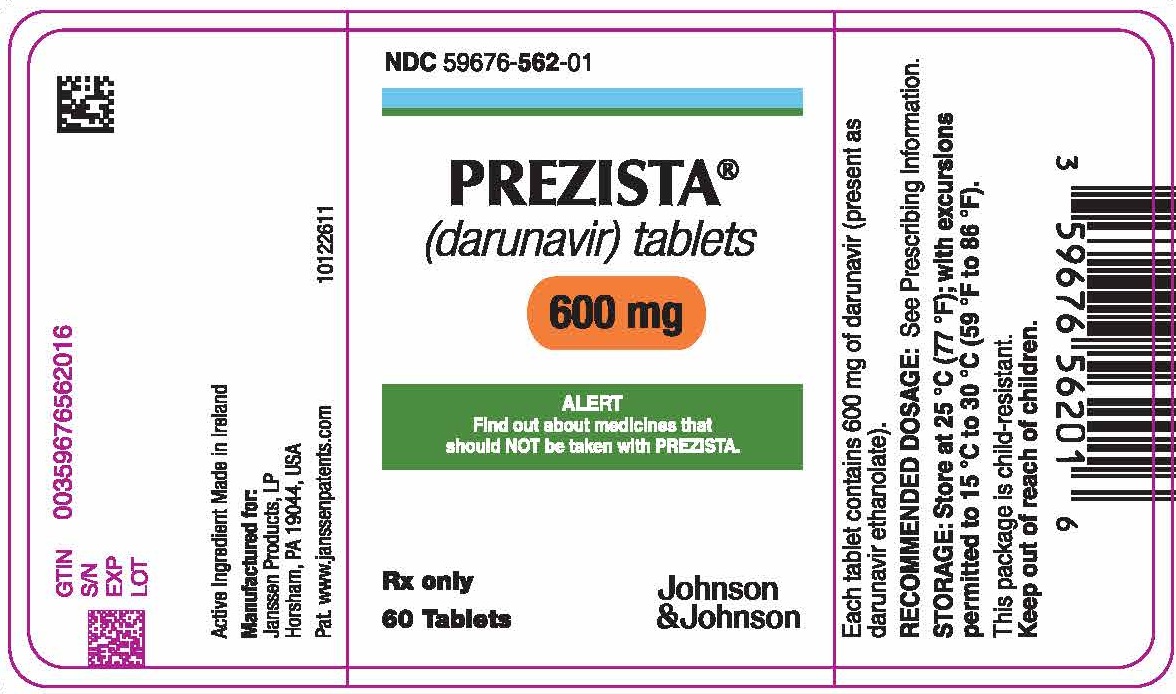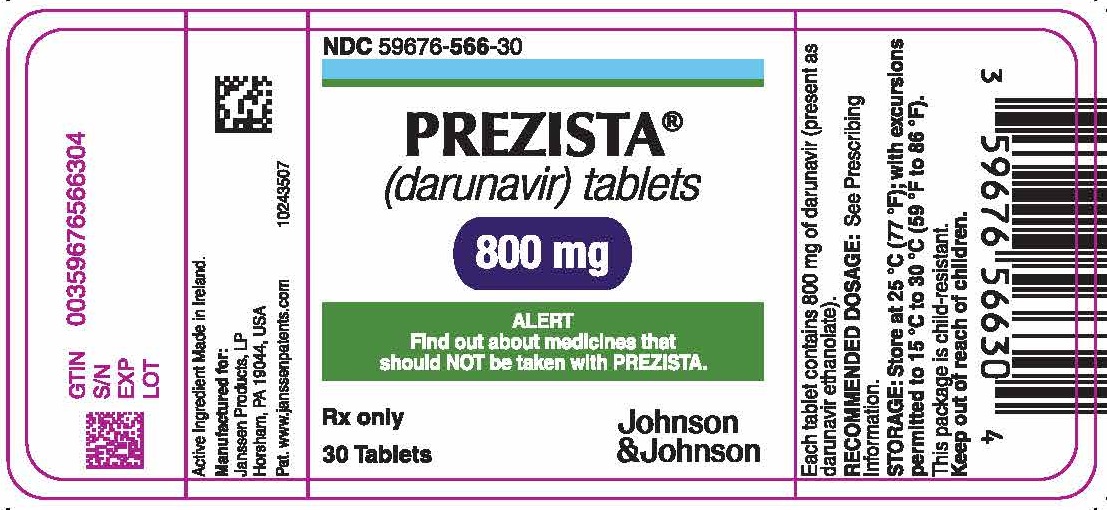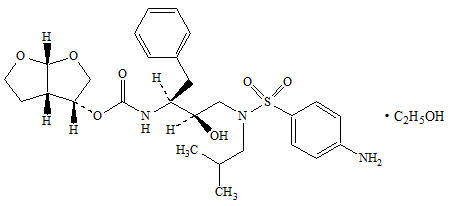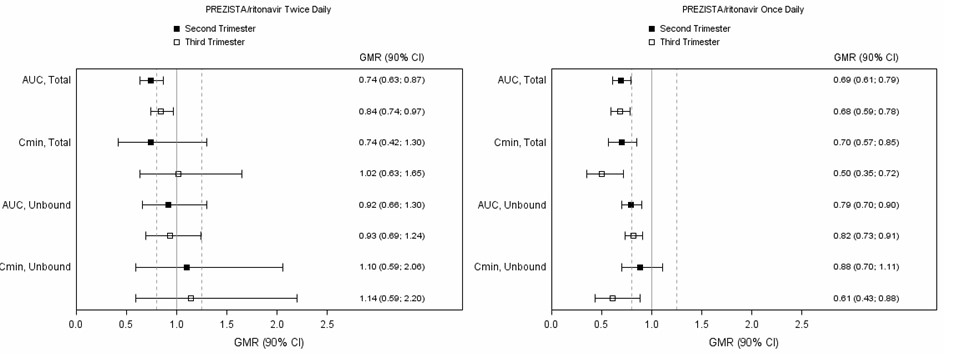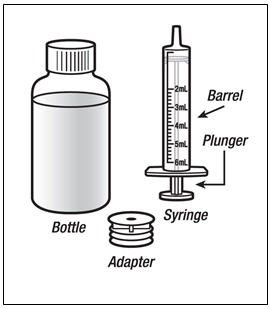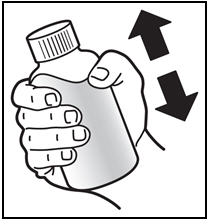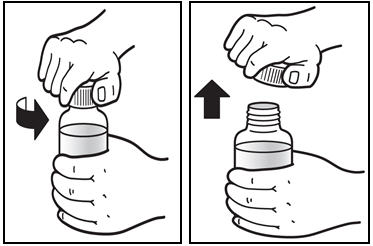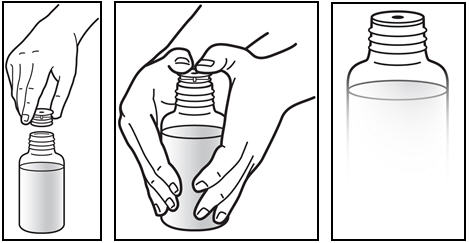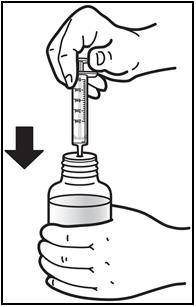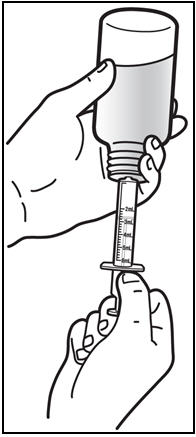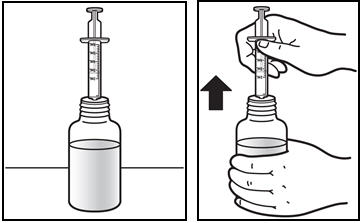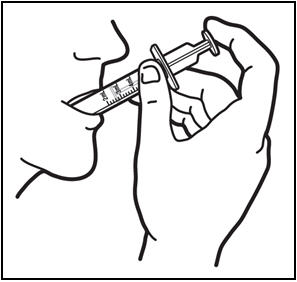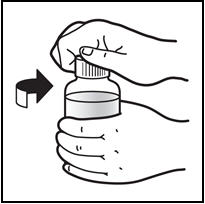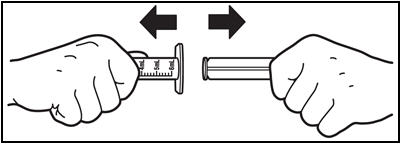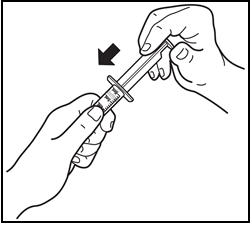 DRUG LABEL: PREZISTA
NDC: 59676-563 | Form: TABLET, FILM COATED
Manufacturer: Janssen Products LP
Category: prescription | Type: HUMAN PRESCRIPTION DRUG LABEL
Date: 20250829

ACTIVE INGREDIENTS: DARUNAVIR ETHANOLATE 75 mg/1 1
INACTIVE INGREDIENTS: SILICON DIOXIDE; CROSPOVIDONE (120 .MU.M); MAGNESIUM STEARATE; MICROCRYSTALLINE CELLULOSE; POLYETHYLENE GLYCOL 3350; POLYVINYL ALCOHOL, UNSPECIFIED; TALC; TITANIUM DIOXIDE

HIGHLIGHTS OF PRESCRIBING INFORMATION

These highlights do not include all the information needed to use PREZISTA safely and effectively. See Full Prescribing Information for PREZISTA.
PREZISTA®(darunavir) oral suspension
PREZISTA®(darunavir) tablet, for oral use
Initial U.S. Approval: 2006

RECENT MAJOR CHANGES

Contraindications (4) | 4/2022

1 INDICATIONS AND USAGE

PREZISTA is a human immunodeficiency virus (HIV-1) protease inhibitor indicated for the treatment of HIV-1 infection in adult and pediatric patients 3 years of age and older. PREZISTA must be co-administered with ritonavir (PREZISTA/ritonavir) and with other antiretroviral agents. (1)

2 DOSAGE AND ADMINISTRATION

- Testing:
  - In treatment-experienced patients, treatment history genotypic and/or phenotypic testing is recommended prior to initiation of therapy with PREZISTA/ritonavir to assess drug susceptibility of the HIV-1 virus (2.1, 12.4)
  - Monitor serum liver chemistry tests before and during therapy with PREZISTA/ritonavir. (2.1, 2.2, 5.2)
- Treatment-naïve adult patients and treatment-experienced adult patients with no darunavir resistance associated substitutions: 800 mg (one 800 mg tablet) taken with ritonavir 100 mg once daily and with food. (2.3)
- Treatment-experienced adult patients with at least one darunavir resistance associated substitution: 600 mg (one 600 mg tablet) taken with ritonavir 100 mg twice daily and with food. (2.3)
- Pregnant patients: 600 mg (one 600 mg tablet) taken with ritonavir 100 mg twice daily and with food. (2.4)
- Pediatric patients (3 to less than 18 years of age and weighing at least 10 kg): dosage of PREZISTA and ritonavir is based on body weight and should not exceed the adult dose. PREZISTA should be taken with ritonavir and with food. (2.5)
- PREZISTA/ritonavir is not recommended for use in patients with severe hepatic impairment. (2.6)

3 DOSAGE FORMS AND STRENGTHS

- Oral suspension: 100 mg per mL (3)
- Tablets: 75 mg, 150 mg, 600 mg, and 800 mg (3)

4 CONTRAINDICATIONS

- Co-administration of PREZISTA/ritonavir is contraindicated with drugs that are highly dependent on CYP3A for clearance and for which elevated plasma concentrations are associated with serious and/or life-threatening events (narrow therapeutic index). (4)

5 WARNINGS AND PRECAUTIONS

- Drug-induced hepatitis (e.g., acute hepatitis, cytolytic hepatitis) has been reported with PREZISTA/ritonavir. Monitor liver function before and during therapy, especially in patients with underlying chronic hepatitis, cirrhosis, or in patients who have pre-treatment elevations of transaminases. Post-marketing cases of liver injury, including some fatalities, have been reported. (5.2)
- Skin reactions ranging from mild to severe, including Stevens-Johnson Syndrome, toxic epidermal necrolysis, drug rash with eosinophilia and systemic symptoms and acute generalized exanthematous pustulosis, have been reported. Discontinue treatment if severe reaction develops. (5.3)
- Use with caution in patients with a known sulfonamide allergy. (5.4)
- Patients may develop new onset diabetes mellitus or hyperglycemia. Initiation or dose adjustments of insulin or oral hypoglycemic agents may be required. (5.6)
- Patients may develop redistribution/accumulation of body fat or immune reconstitution syndrome. (5.7, 5.8)
- Patients with hemophilia may develop increased bleeding events. (5.9)
- PREZISTA/ritonavir is not recommended in pediatric patients below 3 years of age in view of toxicity and mortality observed in juvenile rats dosed with darunavir up to days 23 to 26 of age. (5.10)

6 ADVERSE REACTIONS

- The most common clinical adverse drug reactions to PREZISTA/ritonavir (incidence greater than or equal to 5%) of at least moderate intensity (greater than or equal to Grade 2) were diarrhea, nausea, rash, headache, abdominal pain and vomiting. (6)

To report SUSPECTED ADVERSE REACTIONS, contact Janssen Products, LP at 1-800-JANSSEN (1-800-526-7736) or FDA at 1-800-FDA-1088 or www.fda.gov/medwatch.

7 DRUG INTERACTIONS

- Co-administration of PREZISTA/ritonavir with other drugs can alter the concentrations of other drugs and other drugs may alter the concentrations of darunavir. The potential drug-drug interactions must be considered prior to and during therapy. (4, 5.5, 7, 12.3)

8 USE IN SPECIFIC POPULATIONS

- Pregnancy: Total darunavir exposures were generally lower during pregnancy compared to postpartum period. The reduction in darunavir exposures during pregnancy were greater for once daily dosing compared to the twice daily dosing regimen. (8.1, 12.3)
- Lactation: Women infected with HIV should be instructed not to breastfeed due to the potential for HIV transmission. (8.2)
- Pediatrics: Not recommended for patients less than 3 years of age. (8.4)

FULL PRESCRIBING INFORMATION

1 INDICATIONS AND USAGE

PREZISTA, co-administered with ritonavir (PREZISTA/ritonavir), in combination with other antiretroviral agents, is indicated for the treatment of human immunodeficiency virus (HIV-1) infection in adult and pediatric patients 3 years of age and older [see Use in Specific Populations (8.4)and Clinical Studies (14)] .

2 DOSAGE AND ADMINISTRATION

2.1 Testing Prior to Initiation of PREZISTA/ritonavir

In treatment-experienced patients, treatment history, genotypic and/or phenotypic testing is recommended to assess drug susceptibility of the HIV-1 virus [see Microbiology (12.4)]. Refer to Dosage and Administration (2.3), (2.4)and (2.5)for dosing recommendations.

Appropriate laboratory testing such as serum liver biochemistries should be conducted prior to initiating therapy with PREZISTA/ritonavir [see Warnings and Precautions (5.2)] .

2.2 Monitoring During Treatment with PREZISTA/ritonavir

Patients with underlying chronic hepatitis, cirrhosis, or in patients who have pre-treatment elevations of transaminases should be monitored for elevation in serum liver biochemistries, especially during the first several months of PREZISTA/ritonavir treatment [see Warnings and Precautions (5.2)] .

2.3 Recommended Dosage in Adult Patients

PREZISTA must be co-administered with ritonavir to exert its therapeutic effect. Failure to correctly co-administer PREZISTA with ritonavir will result in plasma levels of darunavir that will be insufficient to achieve the desired antiviral effect and will alter some drug interactions.

Patients who have difficulty swallowing PREZISTA tablets can use the 100 mg per mL PREZISTA oral suspension.

Treatment-Naïve Adult Patients

The recommended oral dose of PREZISTA is 800 mg (one 800 mg tablet or 8 mL of the oral suspension) taken with ritonavir 100 mg (one 100 mg tablet or capsule or 1.25 mL of a 80 mg per mL ritonavir oral solution) once daily and with food. An 8 mL PREZISTA dose should be taken as two 4 mL administrations with the included oral dosing syringe.

Treatment-Experienced Adult Patients

The recommended oral dosage for treatment-experienced adult patients is summarized in Table 1.

Baseline genotypic testing is recommended for dose selection. However, when genotypic testing is not feasible, PREZISTA 600 mg taken with ritonavir 100 mg twice daily is recommended.

Table 1: Recommended PREZISTA/ritonavir Dosage in Treatment-Experienced Adult Patients
 | Formulation and Recommended Dosing
Baseline Resistance | PREZISTA tablets with ritonavir tablets or capsule | PREZISTA oral suspension (100 mg/mL) with ritonavir oral solution (80 mg/mL)
With no darunavir resistance associated substitutions [V11I, V32I, L33F, I47V, I50V, I54L, I54M, T74P, L76V, I84V and L89V] | One 800 mg PREZISTA tablet with one 100 mg ritonavir tablet/capsule, taken once daily with food | 8 mL [An 8 mL darunavir dose should be taken as two 4 mL administrations with the included oral dosing syringe.] PREZISTA oral suspension with 1.25 mL ritonavir oral solution, taken once daily with food
With at least one darunavir resistance associated substitutions , or with no baseline resistance information | One 600 mg PREZISTA tablet with one 100 mg ritonavir tablet/capsule, taken twice daily with food | 6 mL PREZISTA oral suspension with 1.25 mL ritonavir oral solution, taken twice daily with food

2.4 Recommended Dosage During Pregnancy

The recommended dosage in pregnant patients is PREZISTA 600 mg taken with ritonavir 100 mg twice daily with food.

PREZISTA 800 mg taken with ritonavir 100 mg once daily should only be considered in certain pregnant patients who are already on a stable PREZISTA 800 mg with ritonavir 100 mg once daily regimen prior to pregnancy, are virologically suppressed (HIV-1 RNA less than 50 copies per mL), and in whom a change to twice daily PREZISTA 600 mg with ritonavir 100 mg may compromise tolerability or compliance.

2.5 Recommended Dosage in Pediatric Patients (age 3 to less than 18 years)

Healthcare professionals should pay special attention to accurate dose selection of PREZISTA, transcription of the medication order, dispensing information and dosing instruction to minimize risk for medication errors, overdose, and underdose.

Prescribers should select the appropriate dose of PREZISTA/ritonavir for each individual child based on body weight (kg) and should not exceed the recommended dose for adults.

Before prescribing PREZISTA, children weighing greater than or equal to 15 kg should be assessed for the ability to swallow tablets. If a child is unable to reliably swallow a tablet, the use of PREZISTA oral suspension should be considered.

The recommended dose of PREZISTA/ritonavir for pediatric patients (3 to less than 18 years of age and weighing at least 10 kg is based on body weight (see Tables 2, 3, 4, and 5) and should not exceed the recommended adult dose. PREZISTA should be taken with ritonavir and with food.

The recommendations for the PREZISTA/ritonavir dosage regimens were based on pediatric clinical trial data and population pharmacokinetic modeling and simulation [see Use in Specific Populations (8.4)and Clinical Pharmacology (12.3)].

Dosing Recommendations for Treatment-Naïve Pediatric Patients or Antiretroviral Treatment-Experienced Pediatric Patients with No Darunavir Resistance Associated Substitutions

Pediatric Patients Weighing At Least 10 kg but Less than 15 kg

The weight-based dose in antiretroviral treatment-naïve pediatric patients or antiretroviral treatment-experienced pediatric patients with no darunavir resistance associated substitutions is PREZISTA 35 mg/kg once daily with ritonavir 7 mg/kg once daily using the following table:

Table 2: Recommended Dose for Pediatric Patients Weighing 10 kg to Less Than 15 kg Who are Treatment-Naïve or Treatment-Experienced with No Darunavir Resistance Associated Substitutions [darunavir resistance associated substitutions: V11I, V32I, L33F, I47V, I50V, I54M, I54L, T74P, L76V, I84V and L89V]
Body weight (kg) | Formulation: PREZISTA oral suspension (100 mg/mL) and ritonavir oral solution (80 mg/mL)
Body weight (kg) | Dose: once daily with food
Greater than or equal to 10 kg to less than 11 kg | PREZISTA 3.6 mL [The 350 mg, 385 mg, 455 mg and 490 mg darunavir dose for the specified weight groups were rounded up for suspension dosing convenience to 3.6 mL, 4 mL, 4.6 mL and 5 mL, respectively.] (350 mg) with ritonavir 0.8 mL (64 mg)
Greater than or equal to 11 kg to less than 12 kg | PREZISTA 4 mL (385 mg) with ritonavir 0.8 mL (64 mg)
Greater than or equal to 12 kg to less than 13 kg | PREZISTA 4.2 mL (420 mg) with ritonavir 1 mL (80 mg)
Greater than or equal to 13 kg to less than 14 kg | PREZISTA 4.6 mL (455 mg) with ritonavir 1 mL (80 mg)
Greater than or equal to 14 kg to less than 15 kg | PREZISTA 5 mL (490 mg) with ritonavir 1.2 mL (96 mg)

Pediatric Patients Weighing At Least 15 kg

Pediatric patients weighing at least 15 kg can be dosed with PREZISTA oral tablet(s) or suspension using the following table:

Table 3: Recommended Dose for Pediatric Patients Weighing At Least 15 kg Who are Treatment-Naïve or Treatment-Experienced with No Darunavir Resistance Associated Substitutions [darunavir resistance associated substitutions: V11I, V32I, L33F, I47V, I50V, I54M, I54L, T74P, L76V, I84V and L89V]
Body weight (kg) | Formulation: PREZISTA tablet(s) and ritonavir capsules or tablets (100 mg) | Formulation: PREZISTA oral suspension (100 mg/mL) and ritonavir oral solution (80 mg/mL)
Body weight (kg) | Dose: once daily with food | Dose: once daily with food
Greater than or equal to 15 kg to less than 30 kg | PREZISTA 600 mg with ritonavir 100 mg | PREZISTA 6 mL (600 mg) with ritonavir 1.25 mL (100 mg)
Greater than or equal to 30 kg to less than 40 kg | PREZISTA 675 mg with ritonavir 100 mg | PREZISTA 6.8 mL [The 675 mg dose using darunavir tablets for this weight group is rounded up to 6.8 mL for suspension dosing convenience.] [The 6.8 mL and 8 mL darunavir dose should be taken as two (3.4 mL or 4 mL respectively) administrations with the included oral dosing syringe.] (675 mg) with ritonavir 1.25 mL (100 mg)
Greater than or equal to 40 kg | PREZISTA 800 mg with ritonavir 100 mg | PREZISTA 8 mL (800 mg) with ritonavir 1.25 mL (100 mg)

Dosing Recommendations for Treatment-Experienced Pediatric Patients with At Least One Darunavir Resistance Associated Substitutions

Pediatric Patients Weighing At Least 10 kg but Less than 15 kg

The weight-based dose in antiretroviral treatment-experienced pediatric patients with at least one darunavir resistance associated substitution is PREZISTA 20 mg/kg twice daily with ritonavir 3 mg/kg twice daily using the following table:

Table 4: Recommended Dose for Pediatric Patients Weighing 10 kg to Less Than 15 kg Who are Treatment-Experienced with At Least One Darunavir Resistance Associated Substitution [darunavir resistance associated substitutions: V11I, V32I, L33F, I47V, I50V, I54M, I54L, T74P, L76V, I84V and L89V]
Body weight (kg) | Formulation: PREZISTA oral suspension (100 mg/mL) and ritonavir oral solution (80 mg/mL)
Body weight (kg) | Dose: twice daily with food
Greater than or equal to 10 kg to less than 11 kg | PREZISTA 2 mL (200 mg) with ritonavir 0.4 mL (32 mg)
Greater than or equal to 11 kg to less than 12 kg | PREZISTA 2.2 mL (220 mg) with ritonavir 0.4 mL (32 mg)
Greater than or equal to 12 kg to less than 13 kg | PREZISTA 2.4 mL (240 mg) with ritonavir 0.5 mL (40 mg)
Greater than or equal to 13 kg to less than 14 kg | PREZISTA 2.6 mL (260 mg) with ritonavir 0.5 mL (40 mg)
Greater than or equal to 14 kg to less than 15 kg | PREZISTA 2.8 mL (280 mg) with ritonavir 0.6 mL (48 mg)

Pediatric Patients Weighing At Least 15 kg

Pediatric patients weighing at least 15 kg can be dosed with PREZISTA oral tablet(s) or suspension using the following table:

Table 5: Recommended Dose for Pediatric Patients Weighing At Least 15 kg Who are Treatment-Experienced with At Least One Darunavir Resistance Associated Substitution [darunavir resistance associated substitutions: V11I, V32I, L33F, I47V, I50V, I54M, I54L, T74P, L76V, I84V and L89V]
Body weight (kg) | Formulation: PREZISTA tablet(s) and ritonavir tablets, capsules (100 mg) or oral solution (80 mg/mL) | Formulation: PREZISTA oral suspension (100 mg/mL) and ritonavir oral solution (80 mg/mL)
Body weight (kg) | Dose: twice daily with food | Dose: twice daily with food
Greater than or equal to 15 kg to less than 30 kg | PREZISTA 375 mg with ritonavir 0.6 mL (48 mg) | PREZISTA 3.8 mL (375 mg) [The 375 mg and 450 mg dose using darunavir tablets for this weight group is rounded up to 3.8 mL and 4.6 mL for suspension dosing convenience.] with ritonavir 0.6 mL (48 mg)
Greater than or equal to 30 kg to less than 40 kg | PREZISTA 450 mg with ritonavir 0.75 mL (60 mg) | PREZISTA 4.6 mL (450 mg) with ritonavir 0.75 mL (60 mg)
Greater than or equal to 40 kg | PREZISTA 600 mg with ritonavir 100 mg | PREZISTA 6 mL (600 mg) with ritonavir 1.25 mL (100 mg)

The use of PREZISTA/ritonavir in pediatric patients below 3 years of age is not recommended [see Warnings and Precautions (5.10)and Use in Specific Populations (8.4)] .

2.6 Not Recommended in Patients with Severe Hepatic Impairment

No dosage adjustment is required in patients with mild or moderate hepatic impairment. No data are available regarding the use of PREZISTA/ritonavir when co-administered to subjects with severe hepatic impairment; therefore, PREZISTA/ritonavir is not recommended for use in patients with severe hepatic impairment [see Use in Specific Populations (8.6)and Clinical Pharmacology (12.3)] .

3 DOSAGE FORMS AND STRENGTHS

PREZISTA Oral Suspension

PREZISTA 100 mg per mL is supplied as a white to off-white opaque suspension for oral use, containing 100 mg of darunavir per mL of suspension.

PREZISTA Tablets

- 75 mg: white, caplet-shaped, film-coated tablets debossed with "75" on one side and "TMC" on the other side.
- 150 mg: white, oval-shaped, film-coated tablets debossed with "150" on one side and "TMC" on the other side.
- 600 mg: orange, oval-shaped, film-coated tablets debossed with "600MG" on one side and "TMC" on the other side.
- 800 mg: dark red, oval-shaped, film-coated tablets debossed with "800" on one side and "T" on the other side.

4 CONTRAINDICATIONS

Co-administration of PREZISTA/ritonavir is contraindicated with drugs that are highly dependent on CYP3A for clearance and for which elevated plasma concentrations are associated with serious and/or life-threatening events (narrow therapeutic index). Examples of these drugs and other contraindicated drugs (which may lead to reduced efficacy of darunavir) are listed below [see Drug Interactions (7.3)] . Due to the need for co-administration of PREZISTA with ritonavir, please refer to ritonavir prescribing information for a description of ritonavir contraindications.

- Alpha 1-adrenoreceptor antagonist: alfuzosin
- Anti-gout: colchicine, in patients with renal and/or hepatic impairment
- Antimycobacterial: rifampin
- Antipsychotics: lurasidone, pimozide
- Cardiac Disorders: dronedarone, ivabradine, ranolazine
- Ergot derivatives, e.g. dihydroergotamine, ergotamine, methylergonovine
- Herbal product: St. John's wort (Hypericum perforatum)
- Hepatitis C direct acting antiviral: elbasvir/grazoprevir
- Lipid modifying agents: lomitapide, lovastatin, simvastatin
- Opioid Antagonist: naloxegol
- PDE-5 inhibitor: sildenafil when used for treatment of pulmonary arterial hypertension
- Sedatives/hypnotics: orally administered midazolam, triazolam

5 WARNINGS AND PRECAUTIONS

5.1 Importance of Co-administration with Ritonavir

PREZISTA must be co-administered with ritonavir and food to achieve the desired antiviral effect. Failure to administer PREZISTA with ritonavir and food may result in a loss of efficacy of darunavir.

Please refer to ritonavir prescribing information for additional information on precautionary measures.

5.2 Hepatotoxicity

Drug-induced hepatitis (e.g., acute hepatitis, cytolytic hepatitis) has been reported with PREZISTA/ritonavir. During the clinical development program (N=3063), hepatitis was reported in 0.5% of patients receiving combination therapy with PREZISTA/ritonavir. Patients with pre-existing liver dysfunction, including chronic active hepatitis B or C, have an increased risk for liver function abnormalities including severe hepatic adverse events.

Post-marketing cases of liver injury, including some fatalities, have been reported. These have generally occurred in patients with advanced HIV-1 disease taking multiple concomitant medications, having co-morbidities including hepatitis B or C co-infection, and/or developing immune reconstitution syndrome. A causal relationship with PREZISTA/ritonavir therapy has not been established.

Appropriate laboratory testing should be conducted prior to initiating therapy with PREZISTA/ritonavir and patients should be monitored during treatment. Increased AST/ALT monitoring should be considered in patients with underlying chronic hepatitis, cirrhosis, or in patients who have pre-treatment elevations of transaminases, especially during the first several months of PREZISTA/ritonavir treatment.

Evidence of new or worsening liver dysfunction (including clinically significant elevation of liver enzymes and/or symptoms such as fatigue, anorexia, nausea, jaundice, dark urine, liver tenderness, hepatomegaly) in patients on PREZISTA/ritonavir should prompt consideration of interruption or discontinuation of treatment.

5.3 Severe Skin Reactions

During the clinical development program (n=3063), severe skin reactions, accompanied by fever and/or elevations of transaminases in some cases, have been reported in 0.4% of subjects. Stevens-Johnson Syndrome was rarely (less than 0.1%) reported during the clinical development program. During post-marketing experience toxic epidermal necrolysis, drug rash with eosinophilia and systemic symptoms, and acute generalized exanthematous pustulosis have been reported. Discontinue PREZISTA/ritonavir immediately if signs or symptoms of severe skin reactions develop. These can include but are not limited to severe rash or rash accompanied with fever, general malaise, fatigue, muscle or joint aches, blisters, oral lesions, conjunctivitis, hepatitis and/or eosinophilia.

Rash (all grades, regardless of causality) occurred in 10.3% of subjects treated with PREZISTA/ritonavir [see Adverse Reactions (6)] . Rash was mostly mild-to-moderate, often occurring within the first four weeks of treatment and resolving with continued dosing. The discontinuation rate due to rash in subjects using PREZISTA/ritonavir was 0.5%.

Rash occurred more commonly in treatment-experienced subjects receiving regimens containing PREZISTA/ritonavir + raltegravir compared to subjects receiving PREZISTA/ritonavir without raltegravir or raltegravir without PREZISTA/ritonavir. However, rash that was considered drug related occurred at similar rates for all three groups. These rashes were mild to moderate in severity and did not limit therapy; there were no discontinuations due to rash.

5.4 Sulfa Allergy

Darunavir contains a sulfonamide moiety. PREZISTA should be used with caution in patients with a known sulfonamide allergy. In clinical studies with PREZISTA/ritonavir, the incidence and severity of rash were similar in subjects with or without a history of sulfonamide allergy.

5.5 Risk of Serious Adverse Reactions due to Drug Interactions

Initiation of PREZISTA/ritonavir, a CYP3A inhibitor, in patients receiving medications metabolized by CYP3A or initiation of medications metabolized by CYP3A in patients already receiving PREZISTA/ritonavir, may increase plasma concentrations of medications metabolized by CYP3A and reduce plasma concentrations of active metabolite(s) formed by CYP3A.

Initiation of medications that inhibit or induce CYP3A may increase or decrease concentrations of PREZISTA/ritonavir, respectively.

These interactions may lead to:

- Clinically significant adverse reactions, potentially leading to severe, life threatening, or fatal events from greater exposures of concomitant medications.
- Clinically significant adverse reactions from greater exposures of PREZISTA/ritonavir.
- Loss of therapeutic effect of the concomitant medications from lower exposures of active metabolite(s).
- Loss of therapeutic effect of PREZISTA/ritonavir and possible development of resistance from lower exposures of PREZISTA/ritonavir.

See Table 10for steps to prevent or manage these possible and known significant drug interactions, including dosing recommendations [see Drug Interactions (7)] . Consider the potential for drug interactions prior to and during PREZISTA/ritonavir therapy; review concomitant medications during PREZISTA/ritonavir therapy; and monitor for the adverse reactions associated with the concomitant drugs [see Contraindications (4)and Drug Interactions (7)] .

5.6 Diabetes Mellitus/Hyperglycemia

New onset diabetes mellitus, exacerbation of pre-existing diabetes mellitus, and hyperglycemia have been reported during postmarketing surveillance in HIV-infected patients receiving protease inhibitor (PI) therapy. Some patients required either initiation or dose adjustments of insulin or oral hypoglycemic agents for treatment of these events. In some cases, diabetic ketoacidosis has occurred. In those patients who discontinued PI therapy, hyperglycemia persisted in some cases. Because these events have been reported voluntarily during clinical practice, estimates of frequency cannot be made and causal relationships between PI therapy and these events have not been established.

5.7 Fat Redistribution

Redistribution/accumulation of body fat, including central obesity, dorsocervical fat enlargement (buffalo hump), peripheral wasting, facial wasting, breast enlargement, and "cushingoid appearance" have been observed in patients receiving antiretroviral therapy. The mechanism and long-term consequences of these events are currently unknown. A causal relationship has not been established.

5.8 Immune Reconstitution Syndrome

Immune reconstitution syndrome has been reported in patients treated with combination antiretroviral therapy, including PREZISTA. During the initial phase of combination antiretroviral treatment, patients whose immune systems respond may develop an inflammatory response to indolent or residual opportunistic infections (such as Mycobacterium aviuminfection, cytomegalovirus, Pneumocystis jiroveciipneumonia [PCP], or tuberculosis), which may necessitate further evaluation and treatment.

Autoimmune disorders (such as Graves' disease, polymyositis, Guillain-Barré syndrome, and autoimmune hepatitis) have also been reported to occur in the setting of immune reconstitution; however, the time to onset is more variable, and can occur many months after initiation of antiretroviral treatment.

5.9 Hemophilia

There have been reports of increased bleeding, including spontaneous skin hematomas and hemarthrosis in patients with hemophilia type A and B treated with PIs. In some patients, additional factor VIII was given. In more than half of the reported cases, treatment with PIs was continued or reintroduced if treatment had been discontinued. A causal relationship between PI therapy and these episodes has not been established.

5.10 Not Recommended in Pediatric Patients Below 3 Years of Age

PREZISTA/ritonavir in pediatric patients below 3 years of age is not recommended in view of toxicity and mortality observed in juvenile rats dosed with darunavir (from 20 mg/kg to 1000 mg/kg) up to days 23 to 26 of age [see Use in Specific Populations (8.1and 8.4)and Clinical Pharmacology (12.3)] .

6 ADVERSE REACTIONS

The following adverse reactions are discussed in other sections of labeling:

- Hepatotoxicity [see Warnings and Precautions (5.2)]
- Severe Skin Reactions [see Warnings and Precautions (5.3)]
- Diabetes Mellitus/Hyperglycemia [see Warnings and Precautions (5.6)]
- Fat Redistribution [see Warnings and Precautions (5.7)]
- Immune Reconstitution Syndrome [see Warnings and Precautions (5.8)]
- Hemophilia [see Warnings and Precautions (5.9)]

Due to the need for co-administration of PREZISTA with ritonavir, please refer to ritonavir prescribing information for ritonavir-associated adverse reactions.

6.1 Clinical Trials Experience

Because clinical trials are conducted under widely varying conditions, adverse reaction rates observed in the clinical trials of a drug cannot be directly compared to rates in the clinical trials of another drug and may not reflect the rates observed in clinical practice.

Treatment Naïve-Adults: TMC114-C211

The safety assessment is based on all safety data from the Phase 3 trial TMC114-C211 comparing PREZISTA/ritonavir 800/100 mg once daily versus lopinavir/ritonavir 800/200 mg per day in 689 antiretroviral treatment-naïve HIV-1-infected adult subjects. The total mean exposure for subjects in the PREZISTA/ritonavir 800/100 mg once daily arm and in the lopinavir/ritonavir 800/200 mg per day arm was 162.5 and 153.5 weeks, respectively.

The majority of the adverse drug reactions (ADRs) reported during treatment with PREZISTA/ritonavir 800/100 mg once daily were mild in severity. The most common clinical ADRs to PREZISTA/ritonavir 800/100 mg once daily (greater than or equal to 5%) of at least moderate intensity (greater than or equal to Grade 2) were diarrhea, headache, abdominal pain and rash. 2.3% of subjects in the PREZISTA/ritonavir arm discontinued treatment due to ADRs.

ADRs to PREZISTA/ritonavir 800/100 mg once daily of at least moderate intensity (greater than or equal to Grade 2) in antiretroviral treatment-naïve HIV-1-infected adult subjects are presented in Table 6 and subsequent text below the table.

Table 6: Selected Clinical Adverse Drug Reactions to PREZISTA/ritonavir 800/100 mg Once Daily [Excluding laboratory abnormalities reported as ADRs.] of at Least Moderate Intensity (≥Grade 2) Occurring in ≥2% of Antiretroviral Treatment-Naïve HIV-1-Infected Adult Subjects (Trial TMC114-C211)
System organ class, preferred term, % | PREZISTA/ritonavir 800/100 mg once daily + TDF/FTC N=343 | lopinavir/ritonavir 800/200 mg per day + TDF/FTC N=346
Gastrointestinal Disorders
Abdominal pain | 6% | 6%
Diarrhea | 9% | 16%
Nausea | 4% | 4%
Vomiting | 2% | 4%
General Disorders and Administration Site Conditions
Fatigue | <1% | 3%
Metabolism and Nutrition Disorders
Anorexia | 2% | <1%
Nervous System Disorders
Headache | 7% | 6%
Skin and Subcutaneous Tissue Disorders
Rash | 6% | 7%
N=total number of subjects per treatment group; FTC=emtricitabine; TDF=tenofovir disoproxil fumarate

Less Common Adverse Reactions

Treatment-emergent ADRs of at least moderate intensity (greater than or equal to Grade 2) occurring in less than 2% of antiretroviral treatment-naïve subjects receiving PREZISTA/ritonavir 800/100 mg once daily are listed below by body system:

Gastrointestinal Disorders: acute pancreatitis, dyspepsia, flatulence

General Disorders and Administration Site Conditions: asthenia

Hepatobiliary Disorders: acute hepatitis (e.g., acute hepatitis, cytolytic hepatitis, hepatotoxicity)

Immune System Disorders: (drug) hypersensitivity, immune reconstitution syndrome

Metabolism and Nutrition Disorders: diabetes mellitus

Musculoskeletal and Connective Tissue Disorders: myalgia, osteonecrosis

Psychiatric Disorders: abnormal dreams

Skin and Subcutaneous Tissue Disorders: angioedema, pruritus, Stevens-Johnson Syndrome, urticaria

Laboratory Abnormalities

Selected Grade 2 to 4 laboratory abnormalities that represent a worsening from baseline observed in antiretroviral treatment-naïve adult subjects treated with PREZISTA/ritonavir 800/100 mg once daily are presented in Table 7.

Table 7: Grade 2 to 4 Laboratory Abnormalities Observed in Antiretroviral Treatment-Naïve HIV-1-Infected Adult Subjects [Grade 4 data not applicable in Division of AIDS grading scale.] (Trial TMC114-C211)
Laboratory parameter % | Limit | PREZISTA/ritonavir 800/100 mg once daily + TDF/FTC | lopinavir/ritonavir 800/200 mg per day + TDF/FTC
Biochemistry
Alanine Aminotransferase
Grade 2 | >2.5 to ≤5.0 × ULN | 9% | 9%
Grade 3 | >5.0 to ≤10.0 × ULN | 3% | 3%
Grade 4 | >10.0 × ULN | <1% | 3%
Aspartate Aminotransferase
Grade 2 | >2.5 to ≤5.0 × ULN | 7% | 10%
Grade 3 | >5.0 to ≤10.0 × ULN | 4% | 2%
Grade 4 | >10.0 × ULN | 1% | 3%
Alkaline Phosphatase
Grade 2 | >2.5 to ≤5.0 × ULN | 1% | 1%
Grade 3 | >5.0 to ≤10.0 × ULN | 0% | <1%
Grade 4 | >10.0 × ULN | 0% | 0%
Hyperbilirubinemia
Grade 2 | >1.5 to ≤2.5 × ULN | <1% | 5%
Grade 3 | >2.5 to ≤5.0 × ULN | <1% | <1%
Grade 4 | >5.0 × ULN | 0% | 0%
Triglycerides
Grade 2 | 5.65–8.48 mmol/L 500–750 mg/dL | 3% | 10%
Grade 3 | 8.49–13.56 mmol/L 751–1200 mg/dL | 2% | 5%
Grade 4 | >13.56 mmol/L >1200 mg/dL | 1% | 1%
Total Cholesterol
Grade 2 | 6.20–7.77 mmol/L 240–300 mg/dL | 23% | 27%
Grade 3 | >7.77 mmol/L >300 mg/dL | 1% | 5%
Low-Density Lipoprotein Cholesterol
Grade 2 | 4.13–4.90 mmol/L 160–190 mg/dL | 14% | 12%
Grade 3 | ≥4.91 mmol/L ≥191 mg/dL | 9% | 6%
Elevated Glucose Levels
Grade 2 | 6.95–13.88 mmol/L 126–250 mg/dL | 11% | 10%
Grade 3 | 13.89–27.75 mmol/L 251–500 mg/dL | 1% | <1%
Grade 4 | >27.75 mmol/L >500 mg/dL | 0% | 0%
Pancreatic Lipase
Grade 2 | >1.5 to ≤3.0 × ULN | 3% | 2%
Grade 3 | >3.0 to ≤5.0 × ULN | <1% | 1%
Grade 4 | >5.0 × ULN | 0% | <1%
Pancreatic Amylase
Grade 2 | >1.5 to ≤2.0 × ULN | 5% | 2%
Grade 3 | >2.0 to ≤5.0 × ULN | 5% | 4%
Grade 4 | >5.0 × ULN | 0% | <1%
N=total number of subjects per treatment group; FTC=emtricitabine; TDF=tenofovir disoproxil fumarate

Treatment-Experienced Adults: TMC114-C214

The safety assessment is based on all safety data from the Phase 3 trial TMC114-C214 comparing PREZISTA/ritonavir 600/100 mg twice daily versus lopinavir/ritonavir 400/100 mg twice daily in 595 antiretroviral treatment-experienced HIV-1-infected adult subjects. The total mean exposure for subjects in the PREZISTA/ritonavir 600/100 mg twice daily arm and in the lopinavir/ritonavir 400/100 mg twice daily arm was 80.7 and 76.4 weeks, respectively.

The majority of the ADRs reported during treatment with PREZISTA/ritonavir 600/100 mg twice daily were mild in severity. The most common clinical ADRs to PREZISTA/ritonavir 600/100 mg twice daily (greater than or equal to 5%) of at least moderate intensity (greater than or equal to Grade 2) were diarrhea, nausea, rash, abdominal pain and vomiting. 4.7% of subjects in the PREZISTA/ritonavir arm discontinued treatment due to ADRs.

ADRs to PREZISTA/ritonavir 600/100 mg twice daily of at least moderate intensity (greater than or equal to Grade 2) in antiretroviral treatment-experienced HIV-1-infected adult subjects are presented in Table 8 and subsequent text below the table.

Table 8: Selected Clinical Adverse Drug Reactions to PREZISTA/ritonavir 600/100 mg Twice Daily [Excluding laboratory abnormalities reported as ADRs.] of at Least Moderate Intensity (≥Grade 2) Occurring in ≥2% of Antiretroviral Treatment-Experienced HIV-1-Infected Adult Subjects (Trial TMC114-C214)
System organ class, preferred term, % | PREZISTA/ritonavir 600/100 mg twice daily + OBR N=298 | lopinavir/ritonavir 400/100 mg twice daily + OBR N=297
Gastrointestinal Disorders
Abdominal distension | 2% | <1%
Abdominal pain | 6% | 3%
Diarrhea | 14% | 20%
Dyspepsia | 2% | 1%
Nausea | 7% | 6%
Vomiting | 5% | 3%
General Disorders and Administration Site Conditions
Asthenia | 3% | 1%
Fatigue | 2% | 1%
Metabolism and Nutrition Disorders
Anorexia | 2% | 2%
Diabetes mellitus | 2% | <1%
Nervous System Disorders
Headache | 3% | 3%
Skin and Subcutaneous Tissue Disorders
Rash | 7% | 3%
N=total number of subjects per treatment group; OBR=optimized background regimen

Less Common Adverse Reactions

Treatment-emergent ADRs of at least moderate intensity (greater than or equal to Grade 2) occurring in less than 2% of antiretroviral treatment-experienced subjects receiving PREZISTA/ritonavir 600/100 mg twice daily are listed below by body system:

Gastrointestinal Disorders: acute pancreatitis, flatulence

Musculoskeletal and Connective Tissue Disorders: myalgia

Psychiatric Disorders: abnormal dreams

Skin and Subcutaneous Tissue Disorders: pruritus, urticaria

Laboratory Abnormalities

Selected Grade 2 to 4 laboratory abnormalities that represent a worsening from baseline observed in antiretroviral treatment-experienced adult subjects treated with PREZISTA/ritonavir 600/100 mg twice daily are presented in Table 9.

Table 9: Grade 2 to 4 Laboratory Abnormalities Observed in Antiretroviral Treatment-Experienced HIV-1-Infected Adult Subjects [Grade 4 data not applicable in Division of AIDS grading scale.] (Trial TMC114-C214)
Laboratory parameter, % | Limit | PREZISTA/ritonavir 600/100 mg twice daily + OBR | lopinavir/ritonavir 400/100 mg twice daily + OBR
Biochemistry
Alanine Aminotransferase
Grade 2 | >2.5 to ≤5.0 × ULN | 7% | 5%
Grade 3 | >5.0 to ≤10.0 × ULN | 2% | 2%
Grade 4 | >10.0 × ULN | 1% | 2%
Aspartate Aminotransferase
Grade 2 | >2.5 to ≤5.0 × ULN | 6% | 6%
Grade 3 | >5.0 to ≤10.0 × ULN | 2% | 2%
Grade 4 | >10.0 × ULN | <1% | 2%
Alkaline Phosphatase
Grade 2 | >2.5 to ≤5.0 × ULN | <1% | 0%
Grade 3 | >5.0 to ≤10.0 × ULN | <1% | <1%
Grade 4 | >10.0 × ULN | 0% | 0%
Hyperbilirubinemia
Grade 2 | >1.5 to ≤2.5 × ULN | <1% | 2%
Grade 3 | >2.5 to ≤5.0 × ULN | <1% | <1%
Grade 4 | >5.0 × ULN | <1% | 0%
Triglycerides
Grade 2 | 5.65–8.48 mmol/L 500–750 mg/dL | 10% | 11%
Grade 3 | 8.49–13.56 mmol/L 751–1200 mg/dL | 7% | 10%
Grade 4 | >13.56 mmol/L >1200 mg/dL | 3% | 6%
Total Cholesterol
Grade 2 | 6.20–7.77 mmol/L 240–300 mg/dL | 25% | 23%
Grade 3 | >7.77 mmol/L >300 mg/dL | 10% | 14%
Low-Density Lipoprotein Cholesterol
Grade 2 | 4.13–4.90 mmol/L 160–190 mg/dL | 14% | 14%
Grade 3 | ≥4.91 mmol/L ≥191 mg/dL | 8% | 9%
Elevated Glucose Levels
Grade 2 | 6.95–13.88 mmol/L 126–250 mg/dL | 10% | 11%
Grade 3 | 13.89–27.75 mmol/L 251–500 mg/dL | 1% | <1%
Grade 4 | >27.75 mmol/L >500 mg/dL | <1% | 0%
Pancreatic Lipase
Grade 2 | >1.5 to ≤3.0 × ULN | 3% | 4%
Grade 3 | >3.0 to ≤5.0 × ULN | 2% | <1%
Grade 4 | >5.0 × ULN | <1% | 0%
Pancreatic Amylase
Grade 2 | >1.5 to ≤2.0 × ULN | 6% | 7%
Grade 3 | >2.0 to ≤5.0 × ULN | 7% | 3%
Grade 4 | >5.0 × ULN | 0% | 0%
N=total number of subjects per treatment group; OBR=optimized background regimen

Serious ADRs

The following serious ADRs of at least moderate intensity (greater than or equal to Grade 2) occurred in the Phase 2b and Phase 3 trials with PREZISTA/ritonavir: abdominal pain, acute hepatitis, acute pancreatitis, anorexia, asthenia, diabetes mellitus, diarrhea, fatigue, headache, hepatic enzyme increased, hypercholesterolemia, hyperglycemia, hypertriglyceridemia, immune reconstitution syndrome, low density lipoprotein increased, nausea, pancreatic enzyme increased, rash, Stevens-Johnson Syndrome, and vomiting.

Patients Co-Infected with Hepatitis B and/or Hepatitis C Virus

In subjects co-infected with hepatitis B or C virus receiving PREZISTA/ritonavir, the incidence of adverse events and clinical chemistry abnormalities was not higher than in subjects receiving PREZISTA/ritonavir who were not co-infected, except for increased hepatic enzymes [see Warnings and Precautions (5.2)] . The pharmacokinetic exposure in co-infected subjects was comparable to that in subjects without co-infection.

Clinical Trials Experience: Pediatric Patients

PREZISTA/ritonavir has been studied in combination with other antiretroviral agents in 3 Phase 2 trials. TMC114-C212, in which 80 antiretroviral treatment-experienced HIV-1-infected pediatric subjects 6 to less than 18 years of age and weighing at least 20 kg were included, TMC114-C228, in which 21 antiretroviral treatment-experienced HIV-1-infected pediatric subjects 3 to less than 6 years of age and weighing at least 10 kg were included, and TMC114-C230 in which 12 antiretroviral treatment-naïve HIV-1 infected pediatric patients aged from 12 to less than 18 years and weighing at least 40 kg were included. The TMC114-C212 and C228 trials evaluated PREZISTA/ritonavir twice daily dosing and the TMC114-C230 trial evaluated PREZISTA/ritonavir once daily dosing [see Use in Specific Populations (8.4)and Clinical Studies (14.4)] .

Frequency, type, and severity of ADRs in pediatric subjects were comparable to those observed in adults.

TMC114-C212

Clinical ADRs to PREZISTA/ritonavir (all grades, greater than or equal to 3%), were vomiting (13%), diarrhea (11%), abdominal pain (10%), headache (9%), rash (5%), nausea (4%), and fatigue (3%).

Grade 3 or 4 laboratory abnormalities were ALT increased (Grade 3: 3%; Grade 4: 1%), AST increased (Grade 3: 1%), pancreatic amylase increased (Grade 3: 4%, Grade 4: 1%), pancreatic lipase increased (Grade 3: 1%), total cholesterol increased (Grade 3: 1%), and LDL increased (Grade 3: 3%).

TMC114-C228

Clinical ADRs to PREZISTA/ritonavir (all grades, greater than or equal to 5%), were diarrhea (24%), vomiting (19%), rash (19%), abdominal pain (5%), and anorexia (5%).

There were no Grade 3 or 4 laboratory abnormalities considered as ADRs in this trial.

TMC114-C230

Clinical ADRs to PREZISTA/ritonavir (all grades, greater than or equal to 3%), were vomiting (33%), nausea (25%), diarrhea (16.7%), abdominal pain (8.3%), decreased appetite (8.3%), pruritus (8.3%), and rash (8.3%).

There were no Grade 3 or 4 laboratory abnormalities considered as ADRs in this trial.

6.2 Postmarketing Experience

The following adverse reactions have been identified during post-approval use of PREZISTA. Because these reactions are reported voluntarily from a population of uncertain size, it is not always possible to reliably estimate their frequency or establish a causal relationship to drug exposure.

Metabolism and Nutrition Disorders:Redistribution of body fat

Musculoskeletal and Connective Tissue Disorders:Rhabdomyolysis (associated with co-administration with HMG-CoA reductase inhibitors and PREZISTA/ritonavir)

Skin and Subcutaneous Tissue Disorders:Toxic epidermal necrolysis, acute generalized exanthematous pustulosis, drug rash with eosinophilia and systemic symptoms [see Warnings and Precautions (5.3)]

Renal and Urinary Disorders:Crystal nephropathy, crystalluria

7 DRUG INTERACTIONS

7.1 Potential for PREZISTA/ritonavir to Affect Other Drugs

PREZISTA co-administered with ritonavir is an inhibitor of CYP3A, CYP2D6, and P-gp. Co-administration of PREZISTA and ritonavir with drugs that are primarily metabolized by CYP3A and CYP2D6 or are transported by P-gp may result in increased plasma concentrations of such drugs, which could increase or prolong their therapeutic effect and adverse events. PREZISTA co-administered with ritonavir with drugs that have active metabolite(s) formed by CYP3A may result in reduced plasma concentrations of these active metabolite(s), potentially leading to loss of their therapeutic effect (see Table 10).

7.2 Potential for Other Drugs to Affect Darunavir

Darunavir and ritonavir are metabolized by CYP3A. In vitrodata indicate that darunavir may be a P-gp substrate. Drugs that induce CYP3A activity would be expected to increase the clearance of darunavir and ritonavir, resulting in lowered plasma concentrations of darunavir and ritonavir. Co-administration of darunavir and ritonavir and other drugs that inhibit CYP3A, or P-gp may decrease the clearance of darunavir and ritonavir and may result in increased plasma concentrations of darunavir and ritonavir (see Table 10).

7.3 Established and Other Potentially Significant Drug Interactions

Table 10 provides dosing recommendations as a result of drug interactions with PREZISTA/ritonavir. These recommendations are based on either drug interaction studies or predicted interactions due to the expected magnitude of interaction and potential for serious adverse events or loss of efficacy. The table includes examples of potentially significant interactions but is not all inclusive [see Contraindications (4)and Clinical Pharmacology (12.3)] , and therefore the label of each drug that is co-administered with PREZISTA/ritonavir should be consulted for information related to the route of metabolism, interaction pathways, potential risks, and specific actions to be taken with regard to co-administration.

Table 10: Established and Other Potentially Significant Drug Interactions: Alterations in Dose or Regimen May be Recommended Based on Drug Interaction Studies or Predicted Interaction (see Contraindications (4)for a list of examples of contraindicated drugs) [see Clinical Pharmacology (12.3)for Magnitude of Interaction, Tables 15and 16]
Concomitant Drug Class Drug Name Examples | Effect on Concentration of Darunavir Or Concomitant Drug | Clinical Comment
HIV-1-Antiviral Agents: Nucleoside Reverse Transcriptase Inhibitors (NRTIs)
didanosine | ↔ darunavir ↔ didanosine | Didanosine should be administered one hour before or two hours after PREZISTA/ritonavir (which are administered with food).
HIV-1-Antiviral Agents: HIV-Protease Inhibitors (PIs)
indinavir | ↑ darunavir ↑ indinavir | The appropriate dose of indinavir in combination with PREZISTA/ritonavir has not been established.
(The reference regimen for indinavir was indinavir/ritonavir 800/100 mg twice daily.)
lopinavir/ritonavir | ↓ darunavir ↔ lopinavir | Appropriate doses of the combination have not been established. Hence, it is not recommended to co-administer lopinavir/ritonavir and PREZISTA, with or without ritonavir.
saquinavir | ↓ darunavir ↔ saquinavir | Appropriate doses of the combination have not been established. Hence, it is not recommended to co-administer saquinavir and PREZISTA, with or without ritonavir.
Other HIV protease inhibitors, except atazanavir [see Drug Interactions (7.4)] |  | As co-administration with PREZISTA/ritonavir has not been studied, co-administration is not recommended.
HIV-1-Antiviral Agents: CCR5 co-receptor antagonists
maraviroc | ↑ maraviroc | When used in combination with PREZISTA/ritonavir, the dose of maraviroc should be 150 mg twice daily.
Other Agents
Alpha 1-adrenoreceptor antagonist:
alfuzosin | ↑ alfuzosin | Co-administration is contraindicated due to potential for serious and/or life-threatening reactions such as hypotension.
Antibacterial: clarithromycin | ↔ darunavir ↑ clarithromycin | No dose adjustment of the combination is required for patients with normal renal function. For co-administration of clarithromycin and PREZISTA/ritonavir in patients with renal impairment, the following dose adjustments should be considered:; - For subjects with CLcr of 30–60 mL/min, the dose of clarithromycin should be reduced by 50%. - For subjects with CLcr of <30 mL/min, the dose of clarithromycin should be reduced by 75%.
Anticoagulants: Direct Oral Anticoagulants (DOACs)
apixaban | ↑ apixaban | Due to potentially increased bleeding risk, dosing recommendations for co-administration of apixaban with PREZISTA/ritonavir depend on the apixaban dose. Refer to apixaban dosing instructions for co-administration with P-gp and strong CYP3A inhibitors in apixaban prescribing information.
rivaroxaban | ↑ rivaroxaban | Co-administration of PREZISTA/ritonavir and rivaroxaban is not recommended because it may lead to an increased bleeding risk.
dabigatran etexilate edoxaban | ↑ dabigatran ↑ edoxaban | Refer to the dabigatran etexilate or edoxaban prescribing information for recommendations regarding co-administration. The specific recommendations are based on indication, renal function, and effect of the co-administered P-gp inhibitors on the concentration of dabigatran or edoxaban. Clinical monitoring is recommended when a DOAC not affected by CYP3A4 but transported by P-gp, including dabigatran etexilate and edoxaban, is co-administered with PREZISTA/ritonavir.
Other Anticoagulants
warfarin | ↓ warfarin ↔ darunavir | Warfarin concentrations are decreased when co-administered with PREZISTA/ritonavir. It is recommended that the international normalized ratio (INR) be monitored when warfarin is combined with PREZISTA/ritonavir.
Anticonvulsants: carbamazepine | ↔ darunavir ↑ carbamazepine | The dose of either PREZISTA/ritonavir or carbamazepine does not need to be adjusted when initiating co-administration with PREZISTA/ritonavir and carbamazepine. Clinical monitoring of carbamazepine concentrations and its dose titration is recommended to achieve the desired clinical response.
clonazepam | ↑ clonazepam | Clinical monitoring of anticonvulsants that are metabolized by CYP3A is recommended.
phenobarbital, phenytoin | ↔ darunavir ↓ phenytoin ↓ phenobarbital | Phenytoin and phenobarbital levels should be monitored when co-administering with PREZISTA/ritonavir.
Antidepressants: Selective Serotonin Reuptake Inhibitors (SSRIs):
paroxetine, sertraline | ↓ paroxetine ↓ sertraline | If either sertraline or paroxetine is initiated in patients receiving PREZISTA/ritonavir, dose titrating the SSRI based on a clinical assessment of antidepressant response is recommended. Monitor for antidepressant response in patients on a stable dose of sertraline or paroxetine who start treatment with PREZISTA/ritonavir.
Tricyclic Antidepressants (TCAs):
amitriptyline, desipramine, imipramine, nortriptyline | ↑ amitriptyline ↑ desipramine ↑ imipramine ↑ nortriptyline | Use a lower dose of the tricyclic antidepressants and trazodone due to potential increased adverse events such as nausea, dizziness, hypotension and syncope.
Other:trazodone | ↑ trazodone
Antifungals: itraconazole, isavuconazole, ketoconazole, posaconazole | ↑ darunavir ↑ itraconazole ↑ isavuconazole ↑ ketoconazole ↔ posaconazole | Monitor for increased PREZISTA/ritonavir and/or antifungal adverse events with concomitant use of these antifungals. When co-administration is required, the daily dose of ketoconazole or itraconazole should not exceed 200 mg with monitoring for increased antifungal adverse events.
voriconazole | ↓ voriconazole | Voriconazole is not recommended for patients receiving PREZISTA/ritonavir unless an assessment comparing predicted benefit to risk ratio justifies the use of voriconazole.
Anti-gout: colchicine | ↑ colchicine | Co-administration is contraindicated in patients with renal and/or hepatic impairment due to potential for serious and/or life-threatening reactions.; For patients without renal or hepatic impairment:; - Treatment of gout-flares – co-administration of colchicine in patients on PREZISTA/ritonavir: 0.6 mg (1 tablet) × 1 dose, followed by 0.3 mg (half tablet) 1 hour later. Treatment course to be repeated no earlier than 3 days. - Prophylaxis of gout-flares – co-administration of colchicine in patients on PREZISTA/ritonavir: If the original regimen was 0.6 mg twice a day, the regimen should be adjusted to 0.3 mg once a day. If the original regimen was 0.6 mg once a day, the regimen should be adjusted to 0.3 mg once every other day. - Treatment of familial Mediterranean fever – co-administration of colchicine in patients on PREZISTA/ritonavir: maximum daily dose of 0.6 mg (may be given as 0.3 mg twice a day).
Antimalarial: artemether/lumefantrine | ↓ artemether ↓ dihydroartemisinin ↑ lumefantrine ↔ darunavir | The combination of PREZISTA/ritonavir and artemether/lumefantrine can be used without dose adjustments. However, the combination should be used with caution as increased lumefantrine exposure may increase the risk of QT prolongation.
Antimycobacterials:
rifampin | ↓ darunavir | Co-administration is contraindicated due to potential for loss of therapeutic effect and development of resistance.
rifabutin (The reference regimen for rifabutin was 300 mg once daily.) | ↑ darunavir ↑ rifabutin ↑ 25- O-desacetylrifabutin | Dose reduction of rifabutin by at least 75% of the usual dose (300 mg once daily) is recommended (i.e., a maximum dose of 150 mg every other day). Increased monitoring for adverse events is warranted in patients receiving this combination and further dose reduction of rifabutin may be necessary.
rifapentine | ↓ darunavir | Co-administration of PREZISTA/ritonavir with rifapentine is not recommended.
Antineoplastics: dasatinib, nilotinib | ↑ antineoplastics | A decrease in the dosage or an adjustment of the dosing interval of dasatinib and nilotinib may be necessary for patients. Please refer to the dasatinib and nilotinib prescribing information for dosing instructions.
vinblastine, vincristine |  | For vincristine and vinblastine, consideration should be given to temporarily withholding the ritonavir-containing antiretroviral regimen in patients who develop significant hematologic or gastrointestinal side effects when PREZISTA/ritonavir is administered concurrently with vincristine or vinblastine. If the antiretroviral regimen must be withheld for a prolonged period, consideration should be given to initiating a revised regimen that does not include a CYP3A or P-gp inhibitor.
Antipsychotics:
lurasidone | ↑ lurasidone | Co-administration is contraindicated due to potential for serious and/or life-threatening reactions.
pimozide | ↑ pimozide | Co-administration is contraindicated due to potential for serious and/or life-threatening reactions such as cardiac arrhythmias.
quetiapine | ↑ quetiapine | Initiation of PREZISTA with ritonavir in patients taking quetiapine: Consider alternative antiretroviral therapy to avoid increases in quetiapine exposures. If co-administration is necessary, reduce the quetiapine dose to 1/6 of the current dose and monitor for quetiapine-associated adverse reactions. Refer to the quetiapine prescribing information for recommendations on adverse reaction monitoring. Initiation of quetiapine in patients taking PREZISTA with ritonavir: Refer to the quetiapine prescribing information for initial dosing and titration of quetiapine.
e.g. perphenazine, risperidone, thioridazine | ↑ antipsychotics | A decrease in the dose of antipsychotics that are metabolized by CYP3A or CYP2D6 may be needed when co-administered with PREZISTA/ritonavir.
β-Blockers: e.g. carvedilol, metoprolol, timolol | ↑ beta-blockers | Clinical monitoring of patients is recommended. A dose decrease may be needed for these drugs when co-administered with PREZISTA/ritonavir and a lower dose of the beta blocker should be considered.
Calcium Channel Blockers: amlodipine, diltiazem, felodipine, nicardipine, nifedipine, verapamil | ↑ calcium channel blockers | Clinical monitoring of patients is recommended.
Cardiac Disorders:
ranolazine, ivabradine | ↑ ranolazine ↑ ivabradine | Co-administration is contraindicated due to potential for serious and/or life-threatening reactions.
dronedarone | ↑ dronedarone | Co-administration is contraindicated due to potential for serious and/or life-threatening reactions such as cardiac arrhythmias.
Other antiarrhythmics e.g. amiodarone, bepridil, disopyramide, flecainide, lidocaine (systemic), mexiletine, propafenone, quinidine | ↑ antiarrhythmics | Therapeutic concentration monitoring, if available, is recommended for antiarrhythmics when co-administered with PREZISTA/ritonavir.
digoxin | ↑ digoxin | The lowest dose of digoxin should initially be prescribed. The serum digoxin concentrations should be monitored and used for titration of digoxin dose to obtain the desired clinical effect.
Corticosteroids:
dexamethasone (systemic) | ↓ darunavir | Co-administration of PREZISTA/ritonavir with systemic dexamethasone or other systemic corticosteroids that induce CYP3A may result in loss of therapeutic effect and development of resistance to darunavir. Consider alternative corticosteroids.
Corticosteroids primarily metabolized by CYP3A: e.g. betamethasone budesonide ciclesonide fluticasone methylprednisolone mometasone triamcinolone | ↑ corticosteroids | Co-administration with corticosteroids (all routes of administration) of which exposures are significantly increased by strong CYP3A inhibitors can increase the risk for Cushing's syndrome and adrenal suppression. Alternative corticosteroids including beclomethasone, prednisone, and prednisolone (for which PK and/or PD are less affected by strong CYP3A inhibitors relative to other steroids) should be considered, particularly for long term use.
Endothelin receptor antagonist:
bosentan | ↑ bosentan | Co-administration of bosentan in patients on PREZISTA/ritonavir: In patients who have been receiving PREZISTA/ritonavir for at least 10 days, start bosentan at 62.5 mg once daily or every other day based upon individual tolerability.; Co-administration of PREZISTA/ritonavir in patients on bosentan: Discontinue use of bosentan at least 36 hours prior to initiation of PREZISTA/ritonavir. After at least 10 days following the initiation of PREZISTA/ritonavir, resume bosentan at 62.5 mg once daily or every other day based upon individual tolerability.
Ergot derivatives:
e.g. dihydroergotamine, ergotamine, methylergonovine | ↑ ergot derivatives | Co-administration is contraindicated due to potential for serious and/or life-threatening reactions such as acute ergot toxicity characterized by peripheral vasospasm and ischemia of the extremities and other tissues.
Hepatitis C virus (HCV):
Direct-Acting Antivirals: elbasvir/grazoprevir | ↑ elbasvir/grazoprevir | Co-administration is contraindicated due to potential for the increased risk of alanine transaminase (ALT) elevations.
glecaprevir/pibrentasvir | ↑ glecaprevir ↑ pibrentasvir | Co-administration of PREZISTA/ritonavir with glecaprevir/pibrentasvir is not recommended.
Herbal product:
St. John's wort (Hypericum perforatum) | ↓ darunavir | Co-administration is contraindicated due to potential for reduced plasma concentrations of darunavir, which may result in loss of therapeutic effect and development of resistance.
Hormonal contraceptives: |  | Effective alternative (non-hormonal) contraceptive method or a barrier method of contraception is recommended [see Use in Specific Populations (8.3)] .
ethinyl estradiol, norethindrone, drospirenone | ↓ ethinyl estradiol ↓ norethindrone drospirenone: effects unknown | For co-administration with drospirenone, clinical monitoring is recommended due to the potential for hyperkalemia. No data are available to make recommendations on co-administration with other hormonal contraceptives.
Immunosuppressants: e.g. cyclosporine, tacrolimus, sirolimus | ↑ immunosuppressants | Therapeutic concentration monitoring of the immunosuppressive agent is recommended when co-administered with PREZISTA/ritonavir.
Immunosuppressant/neoplastic: everolimus |  | Co-administration of everolimus and PREZISTA/ritonavir is not recommended.
irinotecan |  | Discontinue PREZISTA/ritonavir at least 1 week prior to starting irinotecan therapy. Do not administer PREZISTA/ritonavir with irinotecan unless there are no therapeutic alternatives.
Inhaled beta agonist:
salmeterol | ↑ salmeterol | Co-administration of salmeterol and PREZISTA/ritonavir is not recommended. The combination may result in increased risk of cardiovascular adverse events associated with salmeterol, including QT prolongation, palpitations and sinus tachycardia.
Lipid Modifying Agents:
HMG-CoA reductase inhibitors:
lovastatin, simvastatin | ↑ lovastatin ↑ simvastatin | Co-administration is contraindicated due to potential for serious reactions such as myopathy including rhabdomyolysis.
atorvastatin, pravastatin, rosuvastatin | ↑ HMG-CoA reductase inhibitors | Co-administration of PREZISTA/ritonavir with HMG-Co A reductase inhibitors may lead to adverse events such as myopathy. Titrate atorvastatin, pravastatin or rosuvastatin dose carefully and use the lowest necessary dose while monitoring for adverse events. Do not exceed atorvastatin 20 mg/day.
Other lipid modifying agents:
lomitapide | ↑ lomitapide | Co-administration is contraindicated due to potential for markedly increased transaminases.
Narcotic analgesics metabolized by CYP3A:
e.g. fentanyl, oxycodone | ↑ fentanyl ↑ oxycodone | Careful monitoring of therapeutic effects and adverse reactions associated with CYP3A-metabolized narcotic analgesics (including potentially fatal respiratory depression) is recommended with co-administration.
tramadol | ↑ tramadol | A dose decrease may be needed for tramadol with concomitant use.
Narcotic analgesics/treatment of opioid dependence: buprenorphine, buprenorphine/naloxone | ↔ buprenorphine, naloxone ↑ norbuprenorphine (metabolite) | No dose adjustment for buprenorphine or buprenorphine/naloxone is required with concurrent administration of PREZISTA/ritonavir. Clinical monitoring is recommended if PREZISTA/ritonavir and buprenorphine or buprenorphine/naloxone are co-administered.
methadone | ↓ methadone | No adjustment of methadone dosage is required when initiating co-administration of PREZISTA/ritonavir. However, clinical monitoring is recommended as the dose of methadone during maintenance therapy may need to be adjusted in some patients.
Opioid Antagonist
naloxegol | ↑ naloxegol | Co-administration of PREZISTA/ritonavir and naloxegol is contraindicated due to potential for precipitating opioid withdrawal symptoms.
PDE-5 inhibitors: e.g. avanafil, sildenafil, tadalafil, vardenafil | ↑ PDE-5 inhibitors (only the use of sildenafil at doses used for treatment of erectile dysfunction has been studied with PREZISTA/ritonavir) | Co-administration with PREZISTA/ritonavir may result in an increase in PDE-5 inhibitor-associated adverse events, including hypotension, syncope, visual disturbances and priapism.; Use of PDE-5 inhibitors for pulmonary arterial hypertension (PAH):; Co-administration with sildenafil used for PAH is contraindicated due to potential for sildenafil associated adverse reactions (which include visual disturbances, hypotension, prolonged erection, and syncope). The following dose adjustments are recommended for use of tadalafil with PREZISTA/ritonavir:; - Co-administration of tadalafil in patients on PREZISTA/ritonavir: In patients receiving PREZISTA/ritonavir for at least one week, start tadalafil at 20 mg once daily. Increase to 40 mg once daily based upon individual tolerability. - Co-administration of PREZISTA/ritonavir in patients on tadalafil: Avoid use of tadalafil during the initiation of PREZISTA/ritonavir. Stop tadalafil at least 24 hours prior to starting PREZISTA/ritonavir. After at least one week following the initiation of PREZISTA/ritonavir, resume tadalafil at 20 mg once daily. Increase to 40 mg once daily based upon individual tolerability.; Use of PDE-5 inhibitors for erectile dysfunction: Sildenafil at a single dose not exceeding 25 mg in 48 hours, vardenafil at a single dose not exceeding 2.5 mg dose in 72 hours, or tadalafil at a single dose not exceeding 10 mg dose in 72 hours can be used with increased monitoring for PDE-5 inhibitor-associated adverse events.; Co-administration of PREZISTA/ritonavir and avanafil is not recommended.
Platelet aggregation inhibitor: ticagrelor | ↑ ticagrelor | Co-administration of PREZISTA/ritonavir and ticagrelor is not recommended.
clopidogrel | ↓ clopidogrel active metabolite | Co-administration of PREZISTA/ritonavir and clopidogrel is not recommended due to potential reduction of the antiplatelet activity of clopidogrel.
prasugrel | ↔ prasugrel active metabolite | No dose adjustment is needed when prasugrel is co-administered with PREZISTA/ritonavir.
Proton pump inhibitor: omeprazole | ↓ omeprazole ↔ darunavir | When omeprazole is co-administered with PREZISTA/ritonavir, monitor patients for decreased efficacy of omeprazole. Consider increasing the omeprazole dose in patients whose symptoms are not well controlled; avoid use of more than 40 mg per day of omeprazole.
Sedatives/hypnotics:
orally administered midazolam, triazolam | ↑ midazolam ↑ triazolam | Co-administration is contraindicated due to potential for serious and/or life-threatening reactions such as prolonged or increased sedation or respiratory depression. Triazolam and orally administered midazolam are extensively metabolized by CYP3A. Co-administration of triazolam or orally administered midazolam with PREZISTA may cause large increases in the concentrations of these benzodiazepines.
metabolized by CYP3A e.g. buspirone, diazepam, estazolam, zolpidem | ↑ sedatives/hypnotics | Titration is recommended when co-administering PREZISTA/ritonavir with sedatives/hypnotics metabolized by CYP3A and a lower dose of the sedatives/hypnotics should be considered with monitoring for adverse events.
parenterally administered midazolam |  | Co-administration of parenteral midazolam should be done in a setting which ensures close clinical monitoring and appropriate medical management in case of respiratory depression and/or prolonged sedation. Dosage reduction for midazolam should be considered, especially if more than a single dose of midazolam is administered.
Urinary antispasmodics
fesoterodine | ↑ fesoterodine | When fesoterodine is co-administered with PREZISTA/ritonavir, do not exceed a fesoterodine dose of 4 mg once daily.
solifenacin | ↑ solifenacin | When solifenacin is co-administered with PREZISTA/ritonavir, do not exceed a solifenacin dose of 5 mg once daily.

7.4 Drugs without Clinically Significant Interactions with PREZISTA

No dosage adjustments are recommended when PREZISTA/ritonavir is co-administered with the following medications: atazanavir, dolutegravir, efavirenz, etravirine, nevirapine, nucleoside reverse transcriptase inhibitors (abacavir, emtricitabine, emtricitabine/tenofovir alafenamide, lamivudine, stavudine, tenofovir disoproxil fumarate, zidovudine), pitavastatin, raltegravir, ranitidine, or rilpivirine.

8 USE IN SPECIFIC POPULATIONS

8.1 Pregnancy

Pregnancy Exposure Registry

There is a pregnancy exposure registry that monitors pregnancy outcomes in women exposed to PREZISTA during pregnancy. Healthcare providers are encouraged to register patients by calling the Antiretroviral Pregnancy Registry (APR) 1-800-258-4263.

Risk Summary

Prospective pregnancy data from the APR are not sufficient to adequately assess the risk of birth defects or miscarriage. Available limited data from the APR show no statistically significant difference in the overall risk of major birth defects for darunavir compared with the background rate for major birth defects of 2.7% in a U.S. reference population of the Metropolitan Atlanta Congenital Defects Program (MACDP) [see Data] .

The rate of miscarriage is not reported in the APR. The estimated background rate of miscarriage in clinically recognized pregnancies in the U.S. general population is 15-20%. The background risk of major birth defects and miscarriage for the indicated population is unknown.

Studies in animals did not show evidence of developmental toxicity. Exposures (based on AUC) in rats were 3-fold higher, whereas in mice and rabbits, exposures were lower (less than 1-fold) than human exposures at the recommended daily dose [see Data] .

Clinical Considerations

The recommended dosage in pregnant patients is PREZISTA 600 mg taken with ritonavir 100 mg twice daily with food.

PREZISTA 800 mg taken with ritonavir 100 mg once daily should only be considered in certain pregnant patients who are already on a stable PREZISTA 800 mg with ritonavir 100 mg once daily regimen prior to pregnancy, are virologically suppressed (HIV-1 RNA less than 50 copies per mL), and in whom a change to twice daily PREZISTA 600 mg with ritonavir 100 mg may compromise tolerability or compliance [see Dosage and Administration (2.4)and Clinical Pharmacology (12.3)] .

Data

Human Data

PREZISTA/ritonavir (600/100 mg twice daily or 800/100 mg once daily) in combination with a background regimen was evaluated in a clinical trial of 36 pregnant women during the second and third trimesters, and postpartum. Eighteen subjects were enrolled in each BID and QD treatment arms. Twenty-nine subjects completed the trial through the postpartum period (6–12 weeks after delivery) and 7 subjects discontinued before trial completion, 5 subjects in the BID arm and 2 subjects in the QD arm.

The pharmacokinetic data demonstrate that exposure to darunavir and ritonavir as part of an antiretroviral regimen was lower during pregnancy compared with postpartum (6–12 weeks). Exposure reductions during pregnancy were greater for the once daily regimen as compared to the twice daily regimen [see Clinical Pharmacology (12.3)].

Virologic response was preserved. In the BID arm, the proportion of subjects with HIV-1 RNA <50 copies/mL were 39% (7/18) at baseline, 61% (11/18) through the third trimester visit, and 61% (11/18) through the 6–12 week postpartum visit. Virologic outcomes during the third trimester visit showed HIV-1 RNA ≥50 copies/mL for 11% (2/18) of subjects and were missing for 5 subjects (1 subject discontinued prematurely due to virologic failure). In the QD arm, the proportion of subjects with HIV-1 RNA <50 copies/mL were 61% (11/18) at baseline, 83% (15/18) through the third trimester visit, and 78% (14/18) through the 6–12 week postpartum visit. Virologic outcomes during the third trimester visit showed HIV-1 RNA ≥50 copies/mL for none of the subjects and were missing for 3 subjects (1 subject discontinued prematurely due to virologic failure).

PREZISTA/ritonavir was well tolerated during pregnancy and postpartum. There were no new clinically relevant safety findings compared with the known safety profile of PREZISTA/ritonavir in HIV-1-infected adults.

Among the 31 infants with HIV test results available data, born to the 31 HIV-infected pregnant women who completed trial through delivery or postpartum period, all 31 infants had test results that were negative for HIV-1 at the time of delivery and/or through 16 weeks postpartum. All 31 infants received antiretroviral prophylactic treatment containing zidovudine.

Based on prospective reports to the APR of over 980 exposures to darunavir-containing regimens during pregnancy resulting in live births (including over 660 exposed in the first trimester and over 320 exposed in the second/third trimester), the prevalence of birth defects in live births was 3.6.% (95% CI: 2.3% to 5.3.%) with first trimester exposure to darunavir-containing regimens and 2.5% (95% CI: 1.1% to 4.8%) with second/third trimester exposure to darunavir-containing regimens.

Animal Data

Reproduction studies conducted with darunavir showed no embryotoxicity or teratogenicity in mice (doses up to 1000 mg/kg from gestation day (GD) 6-15 with darunavir alone) and rats (doses up to 1000 mg/kg from GD 7-19 in the presence or absence of ritonavir) as well as in rabbits (doses up to 1000 mg/kg/day from GD 8-20 with darunavir alone). In these studies, darunavir exposures (based on AUC) were higher in rats (3-fold), whereas in mice and rabbits, exposures were lower (less than 1-fold) compared to those obtained in humans at the recommended clinical dose of darunavir boosted with ritonavir.

8.2 Lactation

Risk Summary

The Centers for Disease Control and Prevention recommend that HIV-infected mothers not breastfeed their infants to avoid risking postnatal transmission of HIV.

There are no data on the presence of darunavir in human milk, the effects on the breastfed infant, or the effects on milk production. Darunavir is present in the milk of lactating rats [see Data] . Because of the potential for (1) HIV transmission (in HIV-negative infants), (2) developing viral resistance (in HIV-positive infants) and (3) serious adverse reactions in a breastfed infant, instruct mothers not to breastfeed if they are receiving PREZISTA [see Use in Specific Populations (8.4)] .

Data

Animal Data

Studies in rats (with darunavir alone or with ritonavir) have demonstrated that darunavir is secreted in the milk. In the rat pre- and postnatal development study, a reduction in pup body weight gain was observed due to exposure of pups to drug substances via milk. The maximal maternal plasma exposures achieved with darunavir (up to 1000 mg/kg with ritonavir) were approximately 50% of those obtained in humans at the recommended clinical dose with ritonavir.

8.3 Females and Males of Reproductive Potential

Contraception

Use of PREZISTA may reduce the efficacy of combined hormonal contraceptives and the progestin only pill. Advise patients to use an effective alternative (non-hormonal) contraceptive method or add a barrier method of contraception. For co-administration with drospirenone, clinical monitoring is recommended due to the potential for hyperkalemia [see Drug Interactions (7.3)] .

8.4 Pediatric Use

PREZISTA/ritonavir is not recommended in pediatric patients below 3 years of age because of toxicity and mortality observed in juvenile rats dosed with darunavir (from 20 mg/kg to 1000 mg/kg) up to days 23 to 26 of age [see Warnings and Precautions (5.10), Use in Specific Populations (8.1)and Clinical Pharmacology (12.3)] .

The safety, pharmacokinetic profile, and virologic and immunologic responses of PREZISTA/ritonavir administered twice daily were evaluated in treatment-experienced HIV-1-infected pediatric subjects 3 to less than 18 years of age and weighting at least 10 kg. These subjects were evaluated in clinical trials TMC114-C212 (80 subjects, 6 to less than 18 years of age) and TMC114-228 (21 subjects, 3 to less than 6 years of age) [see Adverse Reactions (6.1), Clinical Pharmacology (12.3)and Clinical Studies (14.4)] . Frequency, type, and severity of adverse drug reactions in pediatric subjects were comparable to those observed in adults [see Adverse Reactions (6.1)] . Refer to Dosage and Administration (2.5)for twice-daily dosing recommendations for pediatric subjects 3 to less than 18 years of age and weighing at least 10 kg.

In clinical trial TMC114-C230, the safety, pharmacokinetic profile and virologic and immunologic responses of PREZISTA/ritonavir administered once daily were evaluated in treatment-naïve HIV-1 infected pediatric subjects 12 to less than 18 years of age (12 subjects) [see Adverse Reactions (6.1), Clinical Pharmacology (12.3)and Clinical Studies (14.4)] . Frequency, type, and severity of adverse drug reactions in pediatric subjects were comparable to those observed in adults [see Adverse Reactions (6.1)] . Once daily dosing recommendations for pediatric patients 3 to less than 12 years of age were derived using population pharmacokinetic modeling and simulation. Although a PREZISTA/ritonavir once daily dosing pediatric trial was not conducted in children less than 12 years of age, there is sufficient clinical safety data to support the predicted PREZISTA exposures for the dosing recommendations in this age group [see Clinical Pharmacology (12.3)] . Please see Dosage and Administration (2.5)for once-daily dosing recommendations for pediatric subjects 3 to less than 18 years of age and weighing at least 10 kg.

Juvenile Animal Data

In a juvenile toxicity study where rats were directly dosed with darunavir (up to 1000 mg/kg), deaths occurred from post-natal day 5 at plasma exposure levels ranging from 0.1 to 1.0 of the human exposure levels. In a 4-week rat toxicology study, when dosing was initiated on post-natal day 23 (the human equivalent of 2 to 3 years of age), no deaths were observed with a plasma exposure (in combination with ritonavir) 2 times the human plasma exposure levels.

8.5 Geriatric Use

Clinical studies of PREZISTA did not include sufficient numbers of patients aged 65 years and over to determine whether they respond differently from younger patients. In general, caution should be exercised in the administration and monitoring of PREZISTA in elderly patients, reflecting the greater frequency of decreased hepatic function, and of concomitant disease or other drug therapy [see Clinical Pharmacology (12.3)] .

8.6 Hepatic Impairment

No dosage adjustment of PREZISTA/ritonavir is necessary for patients with either mild or moderate hepatic impairment. No pharmacokinetic or safety data are available regarding the use of PREZISTA/ritonavir in subjects with severe hepatic impairment. Therefore, PREZISTA/ritonavir is not recommended for use in patients with severe hepatic impairment [see Dosage and Administration (2.6)and Clinical Pharmacology (12.3)] .

8.7 Renal Impairment

Population pharmacokinetic analysis showed that the pharmacokinetics of darunavir were not significantly affected in HIV-infected subjects with moderate renal impairment (CrCL between 30–60 mL/min, n=20). No pharmacokinetic data are available in HIV-1-infected patients with severe renal impairment or end stage renal disease; however, because the renal clearance of darunavir is limited, a decrease in total body clearance is not expected in patients with renal impairment. As darunavir and ritonavir are highly bound to plasma proteins, it is unlikely that they will be significantly removed by hemodialysis or peritoneal dialysis [see Clinical Pharmacology (12.3)] .

10 OVERDOSAGE

Human experience of acute overdose with PREZISTA/ritonavir is limited. No specific antidote is available for overdose with PREZISTA. Treatment of overdose with PREZISTA consists of general supportive measures including monitoring of vital signs and observation of the clinical status of the patient. Since PREZISTA is highly protein bound, dialysis is unlikely to be beneficial in significant removal of the active substance.

11 DESCRIPTION

PREZISTA (darunavir) is an inhibitor of the human immunodeficiency virus (HIV-1) protease.

PREZISTA tablets and oral suspension contain the active ingredient darunavir, (present as darunavir ethanolate) which has the following chemical name: [(1S,2R)-3-[[(4-aminophenyl)sulfonyl](2-methylpropyl)amino]-2-hydroxy-1-(phenylmethyl)propyl]-carbamic acid (3R,3aS,6aR)-hexahydrofuro[2,3-b]furan-3-yl ester monoethanolate. Its molecular formula is C27H37N3O7S ∙ C2H5OH and its molecular weight is 593.73. Darunavir ethanolate has the following structural formula:

Darunavir ethanolate is a white to off-white powder with a solubility of approximately 0.15 mg per mL in water at 20°C.

PREZISTA®100 mg per mL oral suspension is available as a white to off-white opaque suspension for oral administration.

Each mL of the oral suspension contains darunavir 100 mg (present as darunavir ethanolate). In addition, each mL contains the inactive ingredients citric acid monohydrate, hydrochloric acid (for pH adjustment), hydroxypropyl cellulose, masking flavor, methylparaben sodium, microcrystalline cellulose, purified water, sodium carboxymethylcellulose, strawberry cream flavor and sucralose.

PREZISTA®75 mg tablets are available as white, caplet-shaped, film-coated tablets for oral administration. Each 75 mg tablet contains darunavir 75 mg (present as darunavir ethanolate).

PREZISTA®150 mg tablets are available as white, oval-shaped, film-coated tablets for oral administration. Each 150 mg tablet contains darunavir 150 mg (present as darunavir ethanolate).

PREZISTA®600 mg tablets are available as orange, oval-shaped, film-coated tablets for oral administration. Each 600 mg tablet contains darunavir 600 mg (present as darunavir ethanolate).

PREZISTA®800 mg tablets are available as dark red, oval-shaped, film-coated tablets for oral administration. Each 800 mg tablet contains darunavir 800 mg (present as darunavir ethanolate).

During storage, partial conversion from ethanolate to hydrate may occur; however, this does not affect product quality or performance. Each tablet also contains the inactive ingredients colloidal silicon dioxide, crospovidone, magnesium stearate, and microcrystalline cellulose. The 800 mg tablet also contains hypromellose. The 75 and 150 mg tablet film coating, OPADRY®White, contains polyethylene glycol 3350, polyvinyl alcohol-partially hydrolyzed, talc, and titanium dioxide. The 600 mg tablet film coating, OPADRY®Orange, contains FD&C Yellow No. 6, polyethylene glycol 3350, polyvinyl alcohol-partially hydrolyzed, talc, and titanium dioxide. The 800 mg tablet film coating, OPADRY®Dark Red, contains iron oxide red, polyethylene glycol 3350, polyvinyl alcohol-partially hydrolyzed, talc, and titanium dioxide.

All strengths for PREZISTA are expressed in terms of the free form of darunavir.

12 CLINICAL PHARMACOLOGY

12.1 Mechanism of Action

Darunavir is an HIV-1 antiviral drug [see Microbiology (12.4)] .

12.2 Pharmacodynamics

Cardiac Electrophysiology

In a thorough QT/QTc study in 40 healthy subjects, PREZISTA/ritonavir doses of 1.33 times the maximum recommended dose did not affect the QT/QTc interval.

12.3 Pharmacokinetics

Pharmacokinetics in Adults

General

Darunavir is primarily metabolized by CYP3A. Ritonavir inhibits CYP3A, thereby increasing the plasma concentrations of darunavir. When a single dose of PREZISTA 600 mg was given orally in combination with 100 mg ritonavir twice daily, there was an approximate 14-fold increase in the systemic exposure of darunavir. Therefore, PREZISTA should only be used in combination with 100 mg of ritonavir to achieve sufficient exposures of darunavir.

The pharmacokinetics of darunavir, co-administered with low dose ritonavir (100 mg), has been evaluated in healthy adult volunteers and in HIV-1-infected subjects. Table 11 displays the population pharmacokinetic estimates of darunavir after oral administration of PREZISTA/ritonavir 600/100 mg twice daily (based on sparse sampling in 285 patients in trial TMC114-C214, 278 patients in trial TMC114-C229 and 119 patients [integrated data] from trials TMC114-C202 and TMC114-C213) and PREZISTA/ritonavir 800/100 mg once daily (based on sparse sampling in 335 patients in trial TMC114-C211 and 280 patients in trial TMC114-C229) to HIV-1-infected patients.

Table 11: Population Pharmacokinetic Estimates of Darunavir at PREZISTA/ritonavir 800/100 mg Once Daily (Trial TMC114-C211, 48-Week Analysis and Trial TMC114-C229, 48-Week Analysis) and PREZISTA/ritonavir 600/100 mg Twice Daily (Trial TMC114-C214, 48-Week Analysis, Trial TMC114-C229, 48-Week Analysis and Integrated Data from Trials TMC114-C213 and TMC114-C202, Primary 24-Week Analysis)
 | PREZISTA/ritonavir 800/100 mg once daily |  | PREZISTA/ritonavir 600/100 mg twice daily
Parameter | TMC114-C211 N=335 | TMC114-C229 N=280 | TMC114-C214 N=285 | TMC114-C229 N=278 | TMC114-C213 + TMC114-C202 (integrated data) N=119
AUC24h(ng.h/mL) [AUC 24h is calculated as AUC 12h*2.]
Mean ± Standard Deviation | 93026 ± 27050 | 93334 ± 28626 | 116796 ± 33594 | 114302 ± 32681 | 124698 ± 32286
Median (Range) | 87854 (45000–219240) | 87788 (45456–236920) | 111632 (64874–355360) | 109401 (48934–323820) | 123336 (67714–212980)
C0h(ng/mL)
Mean ± Standard Deviation | 2282 ± 1168 | 2160 ± 1201 | 3490 ± 1401 | 3386 ± 1372 | 3578 ± 1151
Median (Range) | 2041 (368–7242) | 1896 (184–7881) | 3307 (1517–13198) | 3197 (250–11865) | 3539 (1255–7368)
N=number of subjects with data

Absorption and Bioavailability

Darunavir, co-administered with 100 mg ritonavir twice daily, was absorbed following oral administration with a Tmaxof approximately 2.5–4 hours. The absolute oral bioavailability of a single 600 mg dose of darunavir alone and after co-administration with 100 mg ritonavir twice daily was 37% and 82%, respectively. In vivodata suggest that PREZISTA/ritonavir is an inhibitor of the P-glycoprotein (P-gp) transporters.

Effects of Food on Oral Absorption

When PREZISTA tablets were administered with food, the Cmaxand AUC of darunavir, co-administered with ritonavir, is approximately 40% higher relative to the fasting state. Within the range of meals studied, darunavir exposure is similar. The total caloric content of the various meals evaluated ranged from 240 Kcal (12 gms fat) to 928 Kcal (56 gms fat).

Distribution

Darunavir is approximately 95% bound to plasma proteins. Darunavir binds primarily to plasma alpha 1-acid glycoprotein (AAG).

Metabolism

In vitroexperiments with human liver microsomes (HLMs) indicate that darunavir primarily undergoes oxidative metabolism. Darunavir is extensively metabolized by CYP enzymes, primarily by CYP3A. A mass balance study in healthy volunteers showed that after a single dose administration of 400 mg^14C-darunavir, co-administered with 100 mg ritonavir, the majority of the radioactivity in the plasma was due to darunavir. At least 3 oxidative metabolites of darunavir have been identified in humans; all showed activity that was at least 90% less than the activity of darunavir against wild-type HIV-1.

Elimination

A mass balance study in healthy volunteers showed that after single dose administration of 400 mg^14C-darunavir, co-administered with 100 mg ritonavir, approximately 79.5% and 13.9% of the administered dose of^14C-darunavir was recovered in the feces and urine, respectively. Unchanged darunavir accounted for approximately 41.2% and 7.7% of the administered dose in feces and urine, respectively. The terminal elimination half-life of darunavir was approximately 15 hours when co-administered with ritonavir. After intravenous administration, the clearance of darunavir, administered alone and co-administered with 100 mg twice daily ritonavir, was 32.8 L/h and 5.9 L/h, respectively.

Special Populations

Hepatic Impairment

Darunavir is primarily metabolized by the liver. The steady-state pharmacokinetic parameters of darunavir were similar after multiple dose co-administration of PREZISTA/ritonavir 600/100 mg twice daily to subjects with normal hepatic function (n=16), mild hepatic impairment (Child-Pugh Class A, n=8), and moderate hepatic impairment (Child-Pugh Class B, n=8). The effect of severe hepatic impairment on the pharmacokinetics of darunavir has not been evaluated [see Dosage and Administration (2.6)and Use in Specific Populations (8.6)] .

Hepatitis B or Hepatitis C Virus Co-infection

The 48-week analysis of the data from Studies TMC114-C211 and TMC114-C214 in HIV-1-infected subjects indicated that hepatitis B and/or hepatitis C virus co-infection status had no apparent effect on the exposure of darunavir.

Renal Impairment

Results from a mass balance study with^14C-PREZISTA/ritonavir showed that approximately 7.7% of the administered dose of darunavir is excreted in the urine as unchanged drug. As darunavir and ritonavir are highly bound to plasma proteins, it is unlikely that they will be significantly removed by hemodialysis or peritoneal dialysis. Population pharmacokinetic analysis showed that the pharmacokinetics of darunavir were not significantly affected in HIV-1-infected subjects with moderate renal impairment (CrCL between 30–60 mL/min, n=20). There are no pharmacokinetic data available in HIV-1-infected patients with severe renal impairment or end stage renal disease [see Use in Specific Populations (8.7)] .

Gender

Population pharmacokinetic analysis showed higher mean darunavir exposure in HIV-1-infected females compared to males. This difference is not clinically relevant.

Race

Population pharmacokinetic analysis of darunavir in HIV-1-infected subjects indicated that race had no apparent effect on the exposure to darunavir.

Geriatric Patients

Population pharmacokinetic analysis in HIV-1-infected subjects showed that darunavir pharmacokinetics are not considerably different in the age range (18 to 75 years) evaluated in HIV-1-infected subjects (n=12, age greater than or equal to 65) [see Use in Specific Populations (8.5)] .

Pediatric Patients

PREZISTA/ritonavir administered twice daily

The pharmacokinetics of darunavir in combination with ritonavir in 93 antiretroviral treatment-experienced HIV-1-infected pediatric subjects 3 to less than 18 years of age and weighing at least 10 kg showed that the administered weight-based dosages resulted in similar darunavir exposure when compared to the darunavir exposure achieved in treatment-experienced adults receiving PREZISTA/ritonavir 600/100 mg twice daily [see Dosage and Administration (2.5)] .

PREZISTA/ritonavir administered once daily

The pharmacokinetics of darunavir in combination with ritonavir in 12 antiretroviral treatment-naïve HIV-1-infected pediatric subjects 12 to less than 18 years of age and weighing at least 40 kg receiving PREZISTA/ritonavir 800/100 mg once daily resulted in similar darunavir exposures when compared to the darunavir exposure achieved in treatment-naïve adults receiving PREZISTA/ritonavir 800/100 mg once daily [see Dosage and Administration (2.5)] .

Based on population pharmacokinetic modeling and simulation, the proposed PREZISTA/ritonavir once daily dosing regimens for pediatric patients 3 to less than 12 years of age is predicted to result in similar darunavir exposures when compared to the darunavir exposures achieved in treatment-naïve adults receiving PREZISTA/ritonavir 800/100 mg once daily [see Dosage and Administration (2.5)] .

The population pharmacokinetic parameters in pediatric subjects with PREZISTA/ritonavir administered once or twice daily are summarized in the table below:

Table 12: Population Pharmacokinetic Estimates of Darunavir Exposure (Trials TMC114-C230, TMC114-C212 and TMC114-C228) Following Administration of Doses in Tables 2 and 3
 | PREZISTA/ritonavir once daily | PREZISTA/ritonavir twice daily
 |  |  | TMC114-C228 [Subjects may have contributed pharmacokinetic data to both the 10 kg to less than 15 kg weight group and the 15 kg to less than 20 kg weight group.]
Parameter | TMC114-C230 [Summary statistics for population pharmacokinetic parameter estimates for DRV after administration of DRV/rtv at 800/100 mg once daily in treatment-naïve HIV-1 infected subjects from 12 to <18 years of age – Week-48 Analyses.] N=12 | TMC114-C212 N=74
Parameter | TMC114-C230 [Summary statistics for population pharmacokinetic parameter estimates for DRV after administration of DRV/rtv at 800/100 mg once daily in treatment-naïve HIV-1 infected subjects from 12 to <18 years of age – Week-48 Analyses.] N=12 | TMC114-C212 N=74 | 10 to less than 15 kg [Calculated from individual pharmacokinetic parameters estimated for Week 2 and Week 4, based on the Week 48 analysis that evaluated a darunavir dose of 20 mg/kg twice daily with ritonavir 3 mg/kg twice daily.] N=10 | 15 to less than 20 kg [The 15 kg to less than 20 kg weight group received 380 mg (3.8 mL) PREZISTA oral suspension twice daily with 48 mg (0.6 mL) ritonavir oral solution twice daily in TMC114-C228. Calculated from individual pharmacokinetic parameters estimated for Week 2 post-dose adjustment visit; Week 24 and Week 48 based on the – Week 48 analysis that evaluated a darunavir dose of 380 mg twice daily.] N=13
AUC24h(ng∙h/mL) [AUC 24h is calculated as AUC 12h*2.])
Mean ± Standard Deviation | 84390 ± 23587 | 126377 ± 34356 | 137896 ± 51420 | 157760 ± 54080
Median (Range) | 86741 (35527–123325) | 127340 (67054–230720) | 124044 (89688–261090) | 132698 (112310–294840)
C0h(ng/mL)
Mean ± Standard Deviation | 2141 ± 865 | 3948 ± 1363 | 4510 ± 2031 | 4848 ± 2143
Median (Range) | 2234 (542–3776) | 3888 (1836–7821) | 4126 (2456–9361) | 3927 (3046–10292)
N=number of subjects with data.

Pregnancy and Postpartum

The exposure to total darunavir and ritonavir after intake of PREZISTA/ritonavir 600/100 mg twice daily and PREZISTA/ritonavir 800/100 mg once daily as part of an antiretroviral regimen was generally lower during pregnancy compared with postpartum (see Table 13, Table 14and Figure 1).

Table 13: Pharmacokinetic Results of Total Darunavir After Administration of PREZISTA/ritonavir at 600/100 mg Twice Daily as Part of an Antiretroviral Regimen, During the 2ndTrimester of Pregnancy, the 3rdTrimester of Pregnancy and Postpartum
Pharmacokinetics of total darunavir (mean ± standard deviation) | 2ndTrimester of pregnancy (n=12) [n=11 for AUC 24h] | 3rdTrimester of pregnancy (n=12) | Postpartum (6–12 Weeks) (n=12)
Cmax, ng/mL | 4668 ± 1097 | 5328 ± 1631 | 6659 ± 2364
AUC24h, ng.h/mL [AUC 24h is calculated as AUC 12h*2.] | 78740 ± 19194 | 91760 ± 34720 | 113780 ± 52680
Cmin, ng/mL | 1922 ± 825 | 2661 ± 1269 | 2851 ± 2216

Table 14: Pharmacokinetic Results of Total Darunavir After Administration of PREZISTA/ritonavir at 800/100 mg Once Daily as Part of an Antiretroviral Regimen, During the 2ndTrimester of Pregnancy, the 3rdTrimester of Pregnancy and Postpartum
Pharmacokinetics of total darunavir (mean ± standard deviation) | 2ndTrimester of pregnancy (n=17) | 3rdTrimester of pregnancy (n=15) | Postpartum (6–12 Weeks) (n=16)
Cmax, ng/mL | 4964 ± 1505 | 5132 ± 1198 | 7310 ± 1704
AUC24h, ng.h/mL | 62289 ± 16234 | 61112 ± 13790 | 92116 ± 29241
Cmin, ng/mL | 1248 ± 542 | 1075 ± 594 | 1473 ± 1141

Due to an increase in the unbound fraction of darunavir during pregnancy compared to postpartum, unbound darunavir exposures were less reduced during pregnancy as compared to postpartum. Exposure reductions during pregnancy were greater for the once daily regimen as compared to the twice daily regimen (see Figure 1).

Figure 1: Pharmacokinetic Results (Within-Subject Comparison) of Total and Unbound Darunavir After Administration of PREZISTA/ritonavir at 600/100 mg Twice Daily or 800/100 mg Once Daily as Part of an Antiretroviral Regimen, During the 2ndand 3rdTrimester of Pregnancy Compared to Postpartum

Legend: 90% CI: 90% confidence interval; GMR: geometric mean ratio. Solid vertical line: ratio of 1.0; dotted vertical lines: reference lines of 0.8 and 1.25.

Drug Interactions

[See also Contraindications (4), Warnings and Precautions (5.5)and Drug Interactions (7). ]

Darunavir co-administered with ritonavir is an inhibitor of CYP3A, CYP2D6, and P-gp. Co-administration of darunavir and ritonavir with drugs primarily metabolized by CYP3A and CYP2D6, or are transported by P-gp, may result in increased plasma concentrations of such drugs, which could increase or prolong their therapeutic effect and adverse events.

Darunavir and ritonavir are metabolized by CYP3A. In vitrodata indicate that darunavir may be a P-gp substrate. Drugs that induce CYP3A activity would be expected to increase the clearance of darunavir and ritonavir, resulting in lowered plasma concentrations of darunavir and ritonavir. Co-administration of darunavir and ritonavir and other drugs that inhibit CYP3A or P-gp may decrease the clearance of darunavir and ritonavir and may result in increased plasma concentrations of darunavir and ritonavir.

Drug interaction studies were performed with darunavir and other drugs likely to be co-administered and some drugs commonly used as probes for pharmacokinetic interactions. The effects of co-administration of darunavir on the AUC, Cmax, and Cminvalues are summarized in Table 15 (effect of other drugs on darunavir) and Table 16 (effect of darunavir on other drugs). For information regarding clinical recommendations, see Drug Interactions (7).

Several interaction studies have been performed with a dose other than the recommended dose of the co-administered drug or darunavir; however, the results are applicable to the recommended dose of the co-administered drug and/or darunavir.

Table 15: Drug Interactions: Pharmacokinetic Parameters for Darunavir in the Presence of Co-Administered Drugs
Co-administered drug | Dose/Schedule |  | N | PK | LS Mean ratio (90% CI) of darunavir Pharmacokinetic parameters with/without co-administered drug no effect =1.00
Co-administered drug | Co-administered Drug | Darunavir/ritonavir | N | PK | Cmax | AUC | Cmin
Co-administration with other HIV protease inhibitors
Atazanavir | 300 mg q.d. [q.d. = once daily] | 400/100 mg b.i.d. [b.i.d. = twice daily] | 13 | ↔ | 1.02 (0.96–1.09) | 1.03 (0.94–1.12) | 1.01 (0.88–1.16)
Indinavir | 800 mg b.i.d. | 400/100 mg b.i.d. | 9 | ↑ | 1.11 (0.98–1.26) | 1.24 (1.09–1.42) | 1.44 (1.13–1.82)
Lopinavir/ritonavir | 400/100 mg b.i.d. | 1200/100 mg b.i.d. [The pharmacokinetic parameters of darunavir in this study were compared with the pharmacokinetic parameters following administration of PREZISTA/ritonavir 600/100 mg twice daily.] | 14 | ↓ | 0.79 (0.67–0.92) | 0.62 (0.53–0.73) | 0.49 (0.39–0.63)
 | 533/133.3 mg b.i.d. | 1200 mg b.i.d. | 15 | ↓ | 0.79 (0.64–0.97) | 0.59 (0.50–0.70) | 0.45 (0.38–0.52)
Saquinavir hard gel capsule | 1000 mg b.i.d. | 400/100 mg b.i.d. | 14 | ↓ | 0.83 (0.75–0.92) | 0.74 (0.63–0.86) | 0.58 (0.47–0.72)
Co-administration with other HIV antiretrovirals
Didanosine | 400 mg q.d. | 600/100 mg b.i.d. | 17 | ↔ | 0.93 (0.86–1.00) | 1.01 (0.95–1.07) | 1.07 (0.95–1.21)
Efavirenz | 600 mg q.d. | 300/100 mg b.i.d. | 12 | ↓ | 0.85 (0.72–1.00) | 0.87 (0.75–1.01) | 0.69 (0.54–0.87)
Etravirine | 200 mg b.i.d. | 600/100 mg b.i.d. | 15 | ↔ | 1.11 (1.01–1.22) | 1.15 (1.05–1.26) | 1.02 (0.90–1.17)
Nevirapine | 200 mg b.i.d. | 400/100 mg b.i.d. | 8 | ↑ | 1.40 [Ratio based on between-study comparison.] (1.14–1.73) | 1.24 (0.97–1.57) | 1.02 (0.79–1.32)
Rilpivirine | 150 mg q.d. | 800/100 mg q.d. | 15 | ↔ | 0.90 (0.81–1.00) | 0.89 (0.81–0.99) | 0.89 (0.68–1.16)
Tenofovir disoproxil fumarate | 300 mg q.d. | 300/100 mg b.i.d. | 12 | ↑ | 1.16 (0.94–1.42) | 1.21 (0.95–1.54) | 1.24 (0.90–1.69)
Co-administration with other drugs
Artemether/lumefantrine | 80/480 mg (6 doses at 0, 8, 24, 36, 48, and 60 hours) | 600/100 mg b.i.d. | 14 | ↔ | 1.00 (0.93–1.07) | 0.96 (0.90–1.03) | 0.87 (0.77–0.98)
Carbamazepine | 200 mg b.i.d. | 600/100 mg b.i.d. | 16 | ↔ | 1.04 (0.93–1.16) | 0.99 (0.90–1.08) | 0.85 (0.73–1.00)
Clarithromycin | 500 mg b.i.d. | 400/100 mg b.i.d. | 17 | ↔ | 0.83 (0.72–0.96) | 0.87 (0.75–1.01) | 1.01 (0.81–1.26)
Ketoconazole | 200 mg b.i.d. | 400/100 mg b.i.d. | 14 | ↑ | 1.21 (1.04–1.40) | 1.42 (1.23–1.65) | 1.73 (1.39–2.14)
Omeprazole | 20 mg q.d. | 400/100 mg b.i.d. | 16 | ↔ | 1.02 (0.95–1.09) | 1.04 (0.96–1.13) | 1.08 (0.93–1.25)
Paroxetine | 20 mg q.d. | 400/100 mg b.i.d. | 16 | ↔ | 0.97 (0.92–1.02) | 1.02 (0.95–1.10) | 1.07 (0.96–1.19)
Pitavastatin | 4 mg q.d. | 800/100 mg q.d. | 27 | ↔ | 1.06 (1.00–1.12) | 1.03 (0.95–1.12) | NA
Ranitidine | 150 mg b.i.d. | 400/100 mg b.i.d. | 16 | ↔ | 0.96 (0.89–1.05) | 0.95 (0.90–1.01) | 0.94 (0.90–0.99)
Rifabutin | 150 mg q.o.d. [q.o.d. = every other day] | 600/100 mg b.i.d. | 11 | ↑ | 1.42 (1.21–1.67) | 1.57 (1.28–1.93) | 1.75 (1.28–2.37)
Sertraline | 50 mg q.d. | 400/100 mg b.i.d. | 13 | ↔ | 1.01 (0.89–1.14) | 0.98 (0.84–1.14) | 0.94 (0.76–1.16)
N = number of subjects with data

Table 16: Drug Interactions: Pharmacokinetic Parameters for Co-Administered Drugs in the Presence of PREZISTA/ritonavir
Co-administered drug | Dose/Schedule |  | N | PK | LS Mean ratio (90% CI) of co-administered drug pharmacokinetic parameters with/without darunavir no effect =1.00
Co-administered drug | Co-administered drug | Darunavir/ritonavir | N | PK | Cmax | AUC | Cmin
Co-administration with other HIV protease inhibitors
Atazanavir | 300 mg q.d. [q.d. = once daily] /100 mg ritonavir q.d. when administered alone | 400/100 mg b.i.d. [b.i.d. = twice daily] | 13 | ↔ | 0.89 (0.78–1.01) | 1.08 (0.94–1.24) | 1.52 (0.99–2.34)
 | 300 mg q.d. when administered with darunavir/ritonavir
Indinavir | 800 mg b.i.d. /100 mg ritonavir b.i.d. when administered alone | 400/100 mg b.i.d. | 9 | ↑ | 1.08 (0.95–1.22) | 1.23 (1.06–1.42) | 2.25 (1.63–3.10)
 | 800 mg b.i.d. when administered with darunavir/ ritonavir
Lopinavir/ritonavir | 400/100 mg b.i.d. [The pharmacokinetic parameters of lopinavir in this study were compared with the pharmacokinetic parameters following administration of lopinavir/ritonavir 400/100 mg twice daily.] | 1200/100 mg b.i.d. | 14 | ↔ | 0.98 (0.78–1.22) | 1.09 (0.86–1.37) | 1.23 (0.90–1.69)
 | 533/133.3 mg b.i.d.. | 1200 mg b.i.d. | 15 | ↔ | 1.11 (0.96–1.30) | 1.09 (0.96–1.24) | 1.13 (0.90–1.42)
Saquinavir hard gel capsule | 1000 mg b.i.d. /100 mg ritonavir b.i.d. when administered alone | 400/100 mg b.i.d. | 12 | ↔ | 0.94 (0.78–1.13) | 0.94 (0.76–1.17) | 0.82 (0.52–1.30)
 | 1000 mg b.i.d. when administered with darunavir/ritonavir
Co-administration with other HIV antiretrovirals
Didanosine | 400 mg q.d. | 600/100 mg b.i.d. | 17 | ↔ | 0.84 (0.59–1.20) | 0.91 (0.75–1.10) | -
Dolutegravir | 30 mg q.d | 600/100 mg b.i.d. | 15 | ↓ | 0.89 (0.83–0.97) | 0.78 (0.72–0.85) | 0.62 [Noted as C τ or C 24 in the dolutegravir U.S. prescribing information] (0.56–0.69)
Dolutegravir | 50 mg q.d. | 600/100 mg b.i.d. with 200 mg b.i.d. etravirine | 9 | ↓ | 0.88 (0.78–1.00) | 0.75 (0.69–0.81) | 0.63 (0.52–0.76)
Efavirenz | 600 mg q.d. | 300/100 mg b.i.d. | 12 | ↑ | 1.15 (0.97–1.35) | 1.21 (1.08–1.36) | 1.17 (1.01–1.36)
Etravirine | 100 mg b.i.d. | 600/100 mg b.i.d. | 14 | ↓ | 0.68 (0.57–0.82) | 0.63 (0.54–0.73) | 0.51 (0.44–0.61)
Nevirapine | 200 mg b.i.d. | 400/100 mg b.i.d. | 8 | ↑ | 1.18 (1.02–1.37) | 1.27 (1.12–1.44) | 1.47 (1.20–1.82)
Rilpivirine | 150 mg q.d. | 800/100 mg q.d. | 14 | ↑ | 1.79 (1.56–2.06) | 2.30 (1.98–2.67) | 2.78 (2.39–3.24)
Tenofovir disoproxil fumarate | 300 mg q.d. | 300/100 mg b.i.d. | 12 | ↑ | 1.24 (1.08–1.42) | 1.22 (1.10–1.35) | 1.37 (1.19–1.57)
Maraviroc | 150 mg b.i.d. | 600/100 mg b.i.d. | 12 | ↑ | 2.29 (1.46–3.59) | 4.05 (2.94–5.59) | 8.00 (6.35–10.1)
 |  | 600/100 mg b.i.d. with 200 mg b.i.d. etravirine | 10 | ↑ | 1.77 (1.20–2.60) | 3.10 (2.57–3.74) | 5.27 (4.51–6.15)
Co-administration with other drugs
Atorvastatin | 40 mg q.d. when administered alone | 300/100 mg b.i.d. | 15 | ↑ | 0.56 (0.48–0.67) | 0.85 (0.76–0.97) | 1.81 (1.37–2.40)
 | 10 mg q.d. when administered with darunavir/ritonavir
Artemether | 80 mg single dose | 600/100 mg b.i.d. | 15 | ↓ | 0.85 (0.68–1.05) | 0.91 (0.78–1.06) | -
Dihydroartemisinin |  |  | 15 | ↑ | 1.06 (0.82–1.39) | 1.12 (0.96–1.30) | -
Artemether | artemether/lumefantrine 80/480 mg (6 doses at 0, 8, 24, 36, 48, and 60 hours) | 600/100 mg b.i.d. | 15 | ↓ | 0.82 (0.61–1.11) | 0.84 (0.69–1.02) | 0.97 (0.90–1.05)
Dihydroartemisinin | artemether/lumefantrine 80/480 mg (6 doses at 0, 8, 24, 36, 48, and 60 hours) |  | 15 | ↓ | 0.82 (0.66–1.01) | 0.82 (0.74–0.91) | 1.00 (0.82–1.22)
Lumefantrine | artemether/lumefantrine 80/480 mg (6 doses at 0, 8, 24, 36, 48, and 60 hours) |  | 15 | ↑ | 1.65 (1.49–1.83) | 2.75 (2.46–3.08) | 2.26 (1.92–2.67)
Buprenorphine/Naloxone | 8/2 mg to 16/4 mg q.d. | 600/100 mg b.i.d. | 17 | ↔ | 0.92 [Ratio is for buprenorphine; mean C max and AUC 24 for naloxone were comparable when buprenorphine/naloxone was administered with or without PREZISTA/ritonavir] (0.79–1.08) | 0.89 (0.78–1.02) | 0.98 (0.82–1.16)
Norbuprenorphine |  |  | 17 | ↑ | 1.36 (1.06–1.74) | 1.46 (1.15–1.85) | 1.71 (1.29–2.27)
Carbamazepine | 200 mg b.i.d. | 600/100 mg b.i.d. | 16 | ↑ | 1.43 (1.34–1.53) | 1.45 (1.35–1.57) | 1.54 (1.41–1.68)
Carbamazepine epoxide |  |  | 16 | ↓ | 0.46 (0.43–0.49) | 0.46 (0.44–0.49) | 0.48 (0.45–0.51)
Clarithromycin | 500 mg b.i.d. | 400/100 mg b.i.d. | 17 | ↑ | 1.26 (1.03–1.54) | 1.57 (1.35–1.84) | 2.74 (2.30–3.26)
Dabigatran etexilate | 150 mg | 800/100 mg single dose | 14 | ↑ | 1.64 (1.21–2.23) | 1.72 (1.33–2.23) | -
 |  | 800/100 mg q.d. [800/100 mg q.d. for 14 days before co-administered with dabigatran etexilate.] | 13 | ↑ | 1.22 (0.89–1.67) | 1.18 (0.90–1.53) | -
Dextromethorphan | 30 mg | 600/100 mg b.i.d. | 12 | ↑ | 2.27 (1.59–3.26) | 2.70 (1.80–4.05) | -
Dextrorphan |  |  |  | ↓ | 0.87 (0.77–0.98) | 0.96 (0.90–1.03) | -
Digoxin | 0.4 mg | 600/100 mg b.i.d. | 8 | ↑ | 1.15 (0.89–1.48) | 1.36 (0.81–2.27) | -
Ethinyl estradiol (EE) | Ortho-Novum 1/35 (35 µg EE /1 mg NE) | 600/100 mg b.i.d. | 11 | ↓ | 0.68 (0.61–0.74) | 0.56 (0.50–0.63) | 0.38 (0.27–0.54)
Norethindrone (NE) |  |  | 11 | ↓ | 0.90 (0.83–0.97) | 0.86 (0.75–0.98) | 0.70 (0.51–0.97)
Ketoconazole | 200 mg b.i.d. | 400/100 mg b.i.d. | 15 | ↑ | 2.11 (1.81–2.44) | 3.12 (2.65–3.68) | 9.68 (6.44–14.55)
R-Methadone | 55–150 mg q.d. | 600/100 mg b.i.d. | 16 | ↓ | 0.76 (0.71–0.81) | 0.84 (0.78–0.91) | 0.85 (0.77–0.94)
Omeprazole | 40 mg single dose | 600/100 mg b.i.d. | 12 | ↓ | 0.66 (0.48–0.90) | 0.58 (0.50–0.66) | -
5-hydroxy omeprazole |  |  |  | ↓ | 0.93 (0.71–1.21) | 0.84 (0.77–0.92) | -
Paroxetine | 20 mg q.d. | 400/100 mg b.i.d. | 16 | ↓ | 0.64 (0.59–0.71) | 0.61 (0.56–0.66) | 0.63 (0.55–0.73)
Pitavastatin | 4 mg q.d. | 800/100 mg q.d. | 27 | ↓ | 0.96 (0.84–1.09) | 0.74 (0.69–0.80) | NA
Pravastatin | 40 mg single dose | 600/100 mg b.i.d. | 14 | ↑ | 1.63 (0.95–2.82) | 1.81 (1.23–2.66) | -
Rifabutin | 150 mg q.o.d. [q.o.d. = every other day] when administered with PREZISTA/ritonavir | 600/100 mg b.i.d. [In comparison to rifabutin 300 mg once daily.] | 11 | ↑ | 0.72 (0.55–0.93) | 0.93 (0.80–1.09) | 1.64 (1.48–1.81)
25- O-desacetyl-rifabutin | 300 mg q.d. when administered alone |  | 11 | ↑ | 4.77 (4.04–5.63) | 9.81 (8.09–11.9) | 27.1 (22.2–33.2)
Sertraline | 50 mg q.d. | 400/100 mg b.i.d. | 13 | ↓ | 0.56 (0.49–0.63) | 0.51 (0.46–0.58) | 0.51 (0.45–0.57)
Sildenafil | 100 mg (single dose) administered alone | 400/100 mg b.i.d. | 16 | ↑ | 0.62 (0.55–0.70) | 0.97 (0.86–1.09) | -
 | 25 mg (single dose)when administered with darunavir/ritonavir
S-warfarin | 10 mg single dose | 600/100 mg b.i.d. | 12 | ↓ | 0.92 (0.86–0.97) | 0.79 (0.73–0.85) | -
7-OH-S-warfarin |  |  | 12 | ↑ | 1.42 (1.24–1.63) | 1.23 (0.97–1.57) | -
N = number of subjects with data;- = no information available

12.4 Microbiology

Mechanism of Action

Darunavir is an inhibitor of the HIV-1 protease. It selectively inhibits the cleavage of HIV-1 encoded Gag-Pol polyproteins in infected cells, thereby preventing the formation of mature virus particles.

Antiviral Activity

Darunavir exhibits activity against laboratory strains and clinical isolates of HIV-1 and laboratory strains of HIV-2 in acutely infected T-cell lines, human peripheral blood mononuclear cells and human monocytes/macrophages with median EC50values ranging from 1.2 to 8.5 nM (0.7 to 5.0 ng/mL). Darunavir demonstrates antiviral activity in cell culture against a broad panel of HIV-1 group M (A, B, C, D, E, F, G), and group O primary isolates with EC50values ranging from less than 0.1 to 4.3 nM. The EC50value of darunavir increases by a median factor of 5.4 in the presence of human serum. Darunavir did not show antagonism when studied in combination with the PIs amprenavir, atazanavir, indinavir, lopinavir, nelfinavir, ritonavir, saquinavir, or tipranavir, the N(t)RTIs abacavir, didanosine, emtricitabine, lamivudine, stavudine, tenofovir, zalcitabine, or zidovudine, the NNRTIs delavirdine, rilpivirine, efavirenz, etravirine, or nevirapine, and the fusion inhibitor enfuvirtide.

Resistance

Cell Culture: HIV-1 isolates with a decreased susceptibility to darunavir have been selected in cell culture and obtained from subjects treated with PREZISTA/ritonavir. Darunavir-resistant virus derived in cell culture from wild-type HIV-1 had 21- to 88-fold decreased susceptibility to darunavir and developed 2 to 4 of the following amino acid substitutions S37D, R41E/T, K55Q, H69Q, K70E, T74S, V77I, or I85V in the protease. Selection in cell culture of darunavir resistant HIV-1 from nine HIV-1 strains harboring multiple PI resistance-associated mutations resulted in the overall emergence of 22 mutations in the protease gene, coding for amino acid substitutions L10F, V11I, I13V, I15V, G16E, L23I, V32I, L33F, S37N, M46I, I47V, I50V, F53L, L63P, A71V, G73S, L76V, V82I, I84V, T91A/S, and Q92R, of which L10F, V32I, L33F, S37N, M46I, I47V, I50V, L63P, A71V, and I84V were the most prevalent. These darunavir-resistant viruses had at least eight protease substitutions and exhibited 50- to 641-fold decreases in darunavir susceptibility with final EC50values ranging from 125 nM to 3461 nM.

Clinical trials of PREZISTA/ritonavir in treatment-experienced subjects: In a pooled analysis of the 600/100 mg PREZISTA/ritonavir twice daily arms of trials TMC114-C213, TMC114-C202, TMC114-C215, and the control arms of etravirine trials TMC125-C206 and TMC125-C216, the amino acid substitutions V32I and I54L or M developed most frequently on PREZISTA/ritonavir in 41% and 25%, respectively, of the treatment-experienced subjects who experienced virologic failure, either by rebound or by never being suppressed (less than 50 copies/mL). Other substitutions that developed frequently in PREZISTA/ritonavir virologic failure isolates occurred at amino acid positions V11I, I15V, L33F, I47V, I50V, and L89V. These amino acid substitutions were associated with decreased susceptibility to darunavir; 90% of the virologic failure isolates had a greater than 7-fold decrease in susceptibility to darunavir at failure. The median darunavir phenotype (fold change from reference) of the virologic failure isolates was 4.3-fold at baseline and 85-fold at failure. Amino acid substitutions were also observed in the protease cleavage sites in the Gag polyprotein of some PREZISTA/ritonavir virologic failure isolates. In trial TMC114-C212 of treatment-experienced pediatric subjects, the amino acid substitutions V32I, I54L and L89M developed most frequently in virologic failures on PREZISTA/ritonavir.

In the 96-week as-treated analysis of the Phase 3 trial TMC114-C214, the percent of virologic failures (never suppressed, rebounders and discontinued before achieving suppression) was 21% (62/298) in the group of subjects receiving PREZISTA/ritonavir 600/100 mg twice daily compared to 32% (96/297) of subjects receiving lopinavir/ritonavir 400/100 mg twice daily. Examination of subjects who failed on PREZISTA/ritonavir 600/100 mg twice daily and had post-baseline genotypes and phenotypes showed that 7 subjects (7/43; 16%) developed PI substitutions on PREZISTA/ritonavir treatment resulting in decreased susceptibility to darunavir. Six of the 7 had baseline PI resistance-associated substitutions and baseline darunavir phenotypes greater than 7. The most common emerging PI substitutions in these virologic failures were V32I, L33F, M46I or L, I47V, I54L, T74P and L76V. These amino acid substitutions were associated with 59- to 839-fold decreased susceptibility to darunavir at failure. Examination of individual subjects who failed in the comparator arm on lopinavir/ritonavir and had post-baseline genotypes and phenotypes showed that 31 subjects (31/75; 41%) developed substitutions on lopinavir treatment resulting in decreased susceptibility to lopinavir (greater than 10-fold) and the most common substitutions emerging on treatment were L10I or F, M46I or L, I47V or A, I54V and L76V. Of the 31 lopinavir/ritonavir virologic failure subjects, 14 had reduced susceptibility (greater than 10-fold) to lopinavir at baseline.

In the 48-week analysis of the Phase 3 trial TMC114-C229, the number of virologic failures (including those who discontinued before suppression after Week 4) was 26% (75/294) in the group of subjects receiving PREZISTA/ritonavir 800/100 mg once daily compared to 19% (56/296) of subjects receiving PREZISTA/ritonavir 600/100 mg twice daily. Examination of isolates from subjects who failed on PREZISTA/ritonavir 800/100 mg once daily and had post-baseline genotypes showed that 8 subjects (8/60; 13%) had isolates that developed IAS-USA defined PI resistance-associated substitutions compared to 5 subjects (5/39; 13%) on PREZISTA/ritonavir 600/100 mg twice daily. Isolates from 2 subjects developed PI resistance associated substitutions associated with decreased susceptibility to darunavir; 1 subject isolate in the PREZISTA/ritonavir 800/100 mg once daily arm, developed substitutions V32I, M46I, L76V and I84V associated with a 24-fold decreased susceptibility to darunavir, and 1 subject isolate in the PREZISTA/ritonavir 600/100 mg twice daily arm developed substitutions L33F and I50V associated with a 40-fold decreased susceptibility to darunavir. In the PREZISTA/ritonavir 800/100 mg once daily and PREZISTA/ritonavir 600/100 mg twice daily groups, isolates from 7 (7/60; 12%) and 4 (4/42; 10%) virologic failures, respectively, developed decreased susceptibility to an NRTI included in the treatment regimen.

Clinical trials of PREZISTA/ritonavir in treatment-naïve subjects: In the 192-week as-treated analysis censoring those who discontinued before Week 4 of the Phase 3 trial TMC114-C211, the percentage of virologic failures (never suppressed, rebounders and discontinued before achieving suppression) was 22% (64/288) in the group of subjects receiving PREZISTA/ritonavir 800/100 mg once daily compared to 29% (76/263) of subjects receiving lopinavir/ritonavir 800/200 mg per day. In the PREZISTA/ritonavir arm, emergent PI resistance-associated substitutions were identified in 11 of the virologic failures with post-baseline genotypic data (n=43). However, none of the darunavir virologic failures had a decrease in darunavir susceptibility (greater than 7-fold change) at failure. In the comparator lopinavir/ritonavir arm, emergent PI resistance-associated substitutions were identified in 17 of the virologic failures with post-baseline genotypic data (n=53), but none of the lopinavir/ritonavir virologic failures had decreased susceptibility to lopinavir (greater than 10-fold change) at failure. The reverse transcriptase M184V substitution and/or resistance to emtricitabine, which was included in the fixed background regimen, was identified in 4 virologic failures from the PREZISTA/ritonavir arm and 7 virologic failures in the lopinavir/ritonavir arm.

Cross-resistance

Cross-resistance among PIs has been observed. Darunavir has a less than 10-fold decreased susceptibility in cell culture against 90% of 3309 clinical isolates resistant to amprenavir, atazanavir, indinavir, lopinavir, nelfinavir, ritonavir, saquinavir and/or tipranavir showing that viruses resistant to these PIs remain susceptible to darunavir.

Darunavir-resistant viruses were not susceptible to amprenavir, atazanavir, indinavir, lopinavir, nelfinavir, ritonavir or saquinavir in cell culture. However, six of nine darunavir-resistant viruses selected in cell culture from PI-resistant viruses showed a fold change in EC50values less than 3 for tipranavir, indicative of limited cross-resistance between darunavir and tipranavir. In trials TMC114-C213, TMC114-C202, and TMC114-C215, 34% (64/187) of subjects in the PREZISTA/ritonavir arm whose baseline isolates had decreased susceptibility to tipranavir (tipranavir fold change greater than 3) achieved less than 50 copies/mL serum HIV-1 RNA levels at Week 96. Of the viruses isolated from subjects experiencing virologic failure on PREZISTA/ritonavir 600/100 mg twice daily (greater than 7-fold change), 41% were still susceptible to tipranavir and 10% were susceptible to saquinavir while less than 2% were susceptible to the other protease inhibitors (amprenavir, atazanavir, indinavir, lopinavir or nelfinavir).

In trial TMC114-C214, the 7 PREZISTA/ritonavir virologic failures with reduced susceptibility to darunavir at failure were also resistant to the approved PIs (fos)amprenavir, atazanavir, lopinavir, indinavir, and nelfinavir at failure. Six of these 7 were resistant to saquinavir and 5 were resistant to tipranavir. Four of these virologic failures were already PI-resistant at baseline.

Cross-resistance between darunavir and nucleoside/nucleotide reverse transcriptase inhibitors, non-nucleoside reverse transcriptase inhibitors, fusion inhibitors, CCR5 co-receptor antagonists, or integrase inhibitors is unlikely because the viral targets are different.

Baseline Genotype/Phenotype and Virologic Outcome Analyses

Genotypic and/or phenotypic analysis of baseline virus may aid in determining darunavir susceptibility before initiation of PREZISTA/ritonavir 600/100 mg twice daily therapy. The effect of baseline genotype and phenotype on virologic response at 96 weeks was analyzed in as-treated analyses using pooled data from the Phase 2b trials (Trials TMC114-C213, TMC114-C202, and TMC114-C215) (n=439). The findings were confirmed with additional genotypic and phenotypic data from the control arms of etravirine trials TMC125-C206 and TMC125-C216 at Week 24 (n=591).

Diminished virologic responses were observed in subjects with 5 or more baseline IAS-defined primary protease inhibitor resistance-associated substitutions (D30N, V32I, L33F, M46I/L, I47A/V, G48V, I50L/V, I54L/M, L76V, V82A/F/L/S/T, I84V, N88S, L90M) (see Table 17).

Table 17: Response to PREZISTA/ritonavir 600/100 mg Twice Daily by Baseline Number of IAS-Defined Primary PI Resistance-Associated Substitutions: As-treated Analysis of Trials TMC114-C213, TMC114-C202, and TMC114-C215
# IAS-defined primary PI substitutions | Proportion of subjects with <50 copies/mL at Week 96 N=439
# IAS-defined primary PI substitutions | Overall | de novoENF | Re-used/No ENF
All | 44% (192/439) | 54% (61/112) | 40% (131/327)
0 – 4 | 50% (162/322) | 58% (49/85) | 48% (113/237)
5 | 22% (16/74) | 47% (9/19) | 13% (7/55)
≥6 | 9% (3/32) | 17% (1/6) | 8% (2/26)
ENF=enfuvirtide

IAS Primary PI Substitutions (2008): D30N, V32I, L33F, M46I/L, I47A/V, G48V, I50L/V, I54L/M, L76V, V82A/F/L/S/T, I84V, N88S, L90M.

The presence at baseline of two or more of the substitutions V11I, V32I, L33F, I47V, I50V, I54L or M, T74P, L76V, I84V or L89V was associated with a decreased virologic response to PREZISTA/ritonavir. In subjects not taking enfuvirtide de novo, the proportion of subjects achieving viral load less than 50 plasma HIV-1 RNA copies/mL at 96 weeks was 59%, 29%, and 12% when the baseline genotype had 0–1, 2 and greater than or equal to 3 of these substitutions, respectively.

Baseline darunavir phenotype (shift in susceptibility relative to reference) was shown to be a predictive factor of virologic outcome. Response rates assessed by baseline darunavir phenotype are shown in Table 18. These baseline phenotype groups are based on the select patient populations in the trials TMC114-C213, TMC114-C202, and TMC114-C215, and are not meant to represent definitive clinical susceptibility breakpoints for PREZISTA/ritonavir. The data are provided to give clinicians information on the likelihood of virologic success based on pre-treatment susceptibility to darunavir.

Table 18: Response (HIV-1 RNA <50 copies/mL at Week 96) to PREZISTA/ritonavir 600/100 mg Twice Daily by Baseline Darunavir Phenotype and by Use of Enfuvirtide: As-treated Analysis of Trials TMC114-C213, TMC114-C202, and TMC114-C215
Baseline DRV phenotype | Proportion of subjects with <50 copies/mL at Week 96 N=417
Baseline DRV phenotype | All | de novoENF | Re-used/No ENF
Overall | 175/417 (42%) | 61/112 (54%) | 131/327 (40%)
0 – 7 | 148/270 (55%) | 44/65 (68%) | 104/205 (51%)
>7 – 20 | 16/53 (30%) | 7/17 (41%) | 9/36 (25%)
>20 | 11/94 (12%) | 6/23 (26%) | 5/71 (7%)
ENF=enfuvirtide

13 NONCLINICAL TOXICOLOGY

13.1 Carcinogenesis, Mutagenesis, Impairment of Fertility

Carcinogenesis and Mutagenesis

Darunavir was evaluated for carcinogenic potential by oral gavage administration to mice and rats up to 104 weeks. Daily doses of 150, 450 and 1000 mg/kg were administered to mice and doses of 50, 150 and 500 mg/kg was administered to rats. A dose-related increase in the incidence of hepatocellular adenomas and carcinomas were observed in males and females of both species as well as an increase in thyroid follicular cell adenomas in male rats. The observed hepatocellular findings in rodents are considered to be of limited relevance to humans. Repeated administration of darunavir to rats caused hepatic microsomal enzyme induction and increased thyroid hormone elimination, which predispose rats, but not humans, to thyroid neoplasms. At the highest tested doses, the systemic exposures to darunavir (based on AUC) were between 0.4- and 0.7-fold (mice) and 0.7- and 1-fold (rats), relative to those observed in humans at the recommended therapeutic doses (600/100 mg twice daily or 800/100 mg once daily).

Darunavir was not mutagenic or genotoxic in a battery of in vitroand in vivoassays including bacterial reserve mutation (Ames), chromosomal aberration in human lymphocytes and in vivomicronucleus test in mice.

Impairment of Fertility

No effects on fertility or early embryonic development were observed with darunavir in rats.

14 CLINICAL STUDIES

14.1 Description of Adult Clinical Trials

The evidence of efficacy of PREZISTA/ritonavir is based on the analyses of 192-week data from a randomized, controlled open-label Phase 3 trial in treatment-naïve (TMC114-C211) HIV-1-infected adult subjects and 96-week data from a randomized, controlled, open-label Phase 3 trial in antiretroviral treatment-experienced (TMC114-C214) HIV-1-infected adult subjects. In addition, 96-week data are included from 2 randomized, controlled Phase 2b trials, TMC114-C213 and TMC114-C202, in antiretroviral treatment-experienced HIV-1-infected adult subjects.

14.2 Treatment-Naïve Adult Subjects

TMC114-C211

TMC114-C211 is a randomized, controlled, open-label Phase 3 trial comparing PREZISTA/ritonavir 800/100 mg once daily versus lopinavir/ritonavir 800/200 mg per day (given as a twice daily or as a once daily regimen) in antiretroviral treatment-naïve HIV-1-infected adult subjects. Both arms used a fixed background regimen consisting of tenofovir disoproxil fumarate 300 mg once daily (TDF) and emtricitabine 200 mg once daily (FTC).

HIV-1-infected subjects who were eligible for this trial had plasma HIV-1 RNA greater than or equal to 5000 copies/mL. Randomization was stratified by screening plasma viral load (HIV-1 RNA less than 100,000 copies/mL or greater than or equal to 100,000 copies/mL) and screening CD4+ cell count (less than 200 cells/mm^3or greater than or equal to 200 cells/mm^3). Virologic response was defined as a confirmed plasma HIV-1 RNA viral load less than 50 copies/mL. Analyses included 689 subjects in trial TMC114-C211 who had completed 192 weeks of treatment or discontinued earlier.

Demographics and baseline characteristics were balanced between the PREZISTA/ritonavir arm and the lopinavir/ritonavir arm (see Table 19). Table 19 compares the demographic and baseline characteristics between subjects in the PREZISTA/ritonavir 800/100 mg once daily arm and subjects in the lopinavir/ritonavir 800/200 mg per day arm in trial TMC114-C211.

Table 19: Demographic and Baseline Characteristics of Subjects in Trial TMC114-C211
 | PREZISTA/ritonavir 800/100 mg once daily + TDF/FTC N=343 | lopinavir/ritonavir 800/200 mg per day + TDF/FTC N=346
Demographic characteristics
Median age (years) (range, years) | 34 (18–70) | 33 (19–68)
Sex
Male | 70% | 70%
Female | 30% | 30%
Race
White | 40% | 45%
Black | 23% | 21%
Hispanic | 23% | 22%
Asian | 13% | 11%
Baseline characteristics
Mean baseline plasma HIV-1 RNA (log10copies/mL) | 4.86 | 4.84
Median baseline CD4+ cell count (cells/mm^3) (range, cells/mm^3) | 228 (4–750) | 218 (2–714)
Percentage of patients with baseline viral load ≥100,000 copies/mL | 34% | 35%
Percentage of patients with baseline CD4+ cell count <200 cells/mm^3 | 41% | 43%
FTC=emtricitabine; TDF=tenofovir disoproxil fumarate

Week 192 outcomes for subjects on PREZISTA/ritonavir 800/100 mg once daily from trial TMC114-C211 are shown in Table 20.

Table 20: Virologic Outcome of Randomized Treatment of Trial TMC114-C211 at 192 Weeks
 | PREZISTA/ritonavir 800/100 mg once daily + TDF/FTC N=343 | lopinavir/ritonavir 800/200 mg per day + TDF/FTC N=346
Virologic success HIV-1 RNA <50 copies/mL | 70% [95% CI: 1.9; 16.1] | 61%
Virologic failure [Includes patients who discontinued prior to Week 192 for lack or loss of efficacy and patients who are ≥50 copies in the 192-week window and patients who had a change in their background regimen that was not permitted by the protocol.] | 12% | 15%
No virologic data at Week 192 window [Window 186–198 Weeks.]
Reasons
Discontinued trial due to adverse event or death [Includes patients who discontinued due to adverse event or death at any time point from Day 1 through the time window if this resulted in no virologic data on treatment during the specified window.] | 5% | 13%
Discontinued trial for other reasons [Other includes: withdrew consent, loss to follow-up, etc., if the viral load at the time of discontinuation was <50 copies/mL.] | 13% | 12%
Missing data during window but on trial | <1% | 0%
N = total number of subjects with data; FTC=emtricitabine; TDF=tenofovir disoproxil fumarate

In trial TMC114-C211 at 192 weeks of treatment, the median increase from baseline in CD4+ cell counts was 258 cells/mm^3in the PREZISTA/ritonavir 800/100 mg once daily arm and 263 cells/mm^3in the lopinavir/ritonavir 800/200 mg per day arm. Of the PREZISTA/ritonavir subjects with a confirmed virologic response of <50 copies/mL at Week 48, 81% remained undetectable at Week 192 versus 68% with lopinavir/ritonavir. In the 192 week analysis, statistical superiority of the PREZISTA/ritonavir regimen over the lopinavir/ritonavir regimen was demonstrated for both ITT and OP populations.

14.3 Treatment-Experienced Adult Subjects

TMC114-C229

TMC114-C229 is a randomized, open-label trial comparing PREZISTA/ritonavir 800/100 mg once daily to PREZISTA/ritonavir 600/100 mg twice daily in treatment-experienced HIV-1-infected patients with screening genotype resistance test showing no darunavir resistance associated substitutions (i.e. V11I, V32I, L33F, I47V, I50V, I54L, I54M, T74P, L76V, I84V, L89V) and a screening viral load of greater than 1,000 HIV-1 RNA copies/mL. Both arms used an optimized background regimen consisting of greater than or equal to 2 NRTIs selected by the investigator.

HIV-1-infected subjects who were eligible for this trial were on a highly active antiretroviral therapy regimen (HAART) for at least 12 weeks. Virologic response was defined as a confirmed plasma HIV-1 RNA viral load less than 50 copies/mL. Analyses included 590 subjects who had completed 48 weeks of treatment or discontinued earlier.

Table 21 compares the demographic and baseline characteristics between subjects in the PREZISTA/ritonavir 800/100 mg once daily arm and subjects in the PREZISTA/ritonavir 600/100 mg twice daily arm in trial TMC114-C229. No imbalances between the 2 arms were noted.

Table 21: Demographic and Baseline Characteristics of Subjects in Trial TMC114-C229
 | PREZISTA/ritonavir 800/100 mg once daily + OBR N=294 | PREZISTA/ritonavir 600/100 mg twice daily + OBR N=296
Demographic characteristics
Median age (years) (range, years) | 40 (18–70) | 40 (18–77)
Sex
Male | 61% | 67%
Female | 39% | 33%
Race
White | 35% | 37%
Black | 28% | 24%
Hispanic | 16% | 20%
Asian | 16% | 14%
Baseline characteristics
Mean baseline plasma HIV-1 RNA (log10copies/mL) | 4.19 | 4.13
Median baseline CD4+ cell count (cells/mm^3) (range, cells/mm^3) | 219 (24–1306) | 236 (44–864)
Percentage of patients with baseline viral load ≥100,000 copies/mL | 13% | 11%
Percentage of patients with baseline CD4+ cell count <200 cells/mm^3 | 43% | 39%
Median darunavir fold change (range) [Based on phenotype (Antivirogram ®).] | 0.50 (0.1–1.8) | 0.50 (0.1–1.9)
Median number of resistance-associated [Johnson VA, Brun-Vézinet F, Clotet B, et al. Update of the drug resistance mutations in HIV-1: December 2008. Top HIV Med 2008; 16(5): 138–145.] :
PI mutations | 3 | 4
NNRTI mutations | 2 | 1
NRTI mutations | 1 | 1
Percentage of subjects susceptible to all available PIs at baseline | 88% | 86%
Percentage of subjects with number of baseline primary protease inhibitor mutations :
0 | 84% | 84%
1 | 8% | 9%
2 | 5% | 4%
≥3 | 3% | 2%
Median number of ARVs previously used [Only counting ARVs, excluding low-dose ritonavir.] :
NRTIs | 3 | 3
NNRTIs | 1 | 1
PIs (excluding low-dose ritonavir) | 1 | 1
OBR=optimized background regimen

Week 48 outcomes for subjects on PREZISTA/ritonavir 800/100 mg once daily from trial TMC114-C229 are shown in Table 22.

Table 22: Virologic Outcome of Randomized Treatment of Trial TMC114-C229 at 48 Weeks
 | PREZISTA/ritonavir 800/100 mg once daily + OBR N=294 | PREZISTA/ritonavir 600/100 mg twice daily + OBR N=296
Virologic success HIV-1 RNA <50 copies/mL | 69% | 69%
Virologic failure [Includes patients who discontinued prior to Week 48 for lack or loss of efficacy, patients who are ≥50 copies in the 48-week window, patients who had a change in their background regimen that was not permitted in the protocol (provided the switch occurred before the earliest onset of an AE leading to permanent stop of trial medication) and patients who discontinued for reasons other than AEs/death and lack or loss of efficacy (provided their last available viral load was detectable (HIV RNA ≥50 copies/mL).] | 26% | 23%
No virologic data at Week 48 window [Window 42–54 Weeks]
Reasons
Discontinued trial due to adverse event or death [Patients who discontinued due to adverse event or death at any time point from Day 1 through the time window if this resulted in no virologic data on treatment during the specified window.] | 3% | 4%
Discontinued trial for other reasons [Other includes: withdrew consent, loss to follow-up, etc., if the viral load at the time of discontinuation was <50 copies/mL.] | 2% | 3%
Missing data during window but on trial | 0% | <1%
N = total number of subjects with data; OBR=optimized background regimen

The mean increase from baseline in CD4+ cell counts was comparable for both treatment arms (108 cells/mm^3and 112 cells/mm^3in the PREZISTA/ritonavir 800/100 mg once daily arm and the PREZISTA/ritonavir 600/100 mg twice daily arm, respectively).

TMC114-C214

TMC114-C214 is a randomized, controlled, open-label Phase 3 trial comparing PREZISTA/ritonavir 600/100 mg twice daily versus lopinavir/ritonavir 400/100 mg twice daily in antiretroviral treatment-experienced, lopinavir/ritonavir-naïve HIV-1-infected adult subjects. Both arms used an optimized background regimen consisting of at least 2 antiretrovirals (NRTIs with or without NNRTIs).

HIV-1-infected subjects who were eligible for this trial had plasma HIV-1 RNA greater than 1000 copies/mL and were on a highly active antiretroviral therapy regimen (HAART) for at least 12 weeks. Virologic response was defined as a confirmed plasma HIV-1 RNA viral load less than 400 copies/mL. Analyses included 595 subjects in trial TMC114-C214 who had completed 96 weeks of treatment or discontinued earlier.

Demographics and baseline characteristics were balanced between the PREZISTA/ritonavir arm and the lopinavir/ritonavir arm (see Table 23). Table 23 compares the demographic and baseline characteristics between subjects in the PREZISTA/ritonavir 600/100 mg twice daily arm and subjects in the lopinavir/ritonavir 400/100 mg twice daily arm in trial TMC114-C214.

Table 23: Demographic and Baseline Characteristics of Subjects in Trial TMC114-C214
 | PREZISTA/ritonavir 600/100 mg twice daily + OBR N=298 | lopinavir/ritonavir 400/100 mg twice daily + OBR N=297
Demographic characteristics
Median age (years) (range, years) | 40 (18–68) | 41 (22–76)
Sex
Male | 77% | 81%
Female | 23% | 19%
Race
White | 54% | 57%
Black | 18% | 17%
Hispanic | 15% | 15%
Asian | 9% | 9%
Baseline characteristics
Mean baseline plasma HIV-1 RNA (log10copies/mL) | 4.33 | 4.28
Median baseline CD4+ cell count (cells/mm^3) (range, cells/mm^3) | 235 (3–831) | 230 (2–1096)
Percentage of patients with baseline viral load ≥100,000 copies/mL | 19% | 17%
Percentage of patients with baseline CD4+ cell count <200 cells/mm^3 | 40% | 40%
Median darunavir fold change (range) | 0.60 (0.10–37.40) | 0.60 (0.1–43.8)
Median lopinavir fold change (range) | 0.70 (0.40–74.40) | 0.80 (0.30–74.50)
Median number of resistance-associated [Johnson VA, Brun-Vezinet F, Clotet B, et al. Update of the drug resistance mutations in HIV-1: Fall 2006. Top HIV Med 2006; 14(3): 125–130.] :
PI mutations | 4 | 4
NNRTI mutations | 1 | 1
NRTI mutations | 2 | 2
Percentage of subjects with number of baseline primary protease inhibitor mutations :
≤1 | 78% | 80%
2 | 8% | 9%
≥3 | 13% | 11%
Median number of ARVs previously used [Only counting ARVs, excluding low-dose ritonavir.] :
NRTIs | 4 | 4
NNRTIs | 1 | 1
PIs (excluding low-dose ritonavir) | 1 | 1
Percentage of subjects resistant [Based on phenotype (Antivirogram ®).] to all available [Commercially available PIs at the time of trial enrollment.] PIs at baseline, excluding darunavir | 2% | 3%
OBR=optimized background regimen

Week 96 outcomes for subjects on PREZISTA/ritonavir 600/100 mg twice daily from trial TMC114-C214 are shown in Table 24.

Table 24: Virologic Outcome of Randomized Treatment of Trial TMC114-C214 at 96 Weeks
 | PREZISTA/ritonavir 600/100 mg twice daily + OBR N=298 | lopinavir/ritonavir 400/100 mg twice daily + OBR N=297
Virologic success HIV-1 RNA <50 copies/mL | 58% | 52%
Virologic failure [Includes patients who discontinued prior to Week 96 for lack or loss of efficacy and patients who are ≥50 copies in the 96-week window and patients who had a change in their OBR that was not permitted by the protocol.] | 26% | 33%
No virologic data at Week 96 window [Window 90–102 Weeks.]
Reasons
Discontinued trial due to adverse event or death [Includes patients who discontinued due to adverse event or death at any time point from Day 1 through the time window if this resulted in no virologic data on treatment during the specified window.] | 7% | 8%
Discontinued trial for other reasons [Other includes: withdrew consent, loss to follow-up, etc., if the viral load at the time of discontinuation was <50 copies/mL.] | 8% | 7%
Missing data during window but on trial | 1% | <1%
N = total number of subjects with data; OBR=optimized background regimen

In trial TMC114-C214 at 96 weeks of treatment, the median increase from baseline in CD4+ cell counts was 81 cells/mm^3in the PREZISTA/ritonavir 600/100 mg twice daily arm and 93 cells/mm^3in the lopinavir/ritonavir 400/100 mg twice daily arm.

TMC114-C213 and TMC114-C202

TMC114-C213 and TMC114-C202 are randomized, controlled, Phase 2b trials in adult subjects with a high level of PI resistance consisting of 2 parts: an initial partially-blinded, dose-finding part and a second long-term part in which all subjects randomized to PREZISTA/ritonavir received the recommended dose of 600/100 mg twice daily.

HIV-1-infected subjects who were eligible for these trials had plasma HIV-1 RNA greater than 1000 copies/mL, had prior treatment with PI(s), NNRTI(s) and NRTI(s), had at least one primary PI mutation (D30N, M46I/L, G48V, I50L/V, V82A/F/S/T, I84V, L90M) at screening, and were on a stable PI-containing regimen at screening for at least 8 weeks. Randomization was stratified by the number of PI mutations, screening viral load, and the use of enfuvirtide.

The virologic response rate was evaluated in subjects receiving PREZISTA/ritonavir plus an OBR versus a control group receiving an investigator-selected PI(s) regimen plus an OBR. Prior to randomization, PI(s) and OBR were selected by the investigator based on genotypic resistance testing and prior ARV history. The OBR consisted of at least 2 NRTIs with or without enfuvirtide. Selected PI(s) in the control arm included: lopinavir in 36%, (fos)amprenavir in 34%, saquinavir in 35% and atazanavir in 17%; 98% of control subjects received a ritonavir boosted PI regimen out of which 23% of control subjects used dual-boosted PIs. Approximately 47% of all subjects used enfuvirtide, and 35% of the use was in subjects who were ENF-naïve. Virologic response was defined as a decrease in plasma HIV-1 RNA viral load of at least 1 log10versus baseline.

In the pooled analysis for TMC114-C213 and TMC114-C202, demographics and baseline characteristics were balanced between the PREZISTA/ritonavir arm and the comparator PI arm (see Table 25). Table 25 compares the demographic and baseline characteristics between subjects in the PREZISTA/ritonavir 600/100 mg twice daily arm and subjects in the comparator PI arm in the pooled analysis of trials TMC114-C213 and TMC114-C202.

Table 25: Demographic and Baseline Characteristics of Subjects in the Trials TMC114-C213 and TMC114-C202 (Pooled Analysis)
 | PREZISTA/ritonavir 600/100 mg twice daily + OBR | Comparator PI(s) + OBR
 | N=131 | N=124
Demographic characteristics
Median age (years) (range, years) | 43 (27–73) | 44 (25–65)
Sex
Male | 89% | 88%
Female | 11% | 12%
Race
White | 81% | 73%
Black | 10% | 15%
Hispanic | 7% | 8%
Baseline characteristics
Mean baseline plasma HIV-1 RNA (log10copies/mL) | 4.61 | 4.49
Median baseline CD4+ cell count (cells/mm^3) (range, cells/mm^3) | 153 (3–776) | 163 (3–1274)
Percentage of patients with baseline viral load >100,000 copies/mL | 24% | 29%
Percentage of patients with baseline CD4+ cell count <200 cells/mm^3 | 67% | 58%
Median darunavir fold change | 4.3 | 3.3
Median number of resistance-associated [Johnson VA, Brun-Vezinet F, Clotet B, et al. Update of the drug resistance mutations in HIV-1: Fall 2006. Top HIV Med 2006; 14(3): 125–130.] :
PI mutations | 12 | 12
NNRTI mutations | 1 | 1
NRTI mutations | 5 | 5
Percentage of subjects with number of baseline primary protease inhibitor mutations :
≤1 | 8% | 9%
2 | 22% | 21%
≥3 | 70% | 70%
Median number of ARVs previously used [Based on phenotype (Antivirogram ®).] :
NRTIs | 6 | 6
NNRTIs | 1 | 1
PIs (excluding low-dose ritonavir) | 5 | 5
Percentage of subjects resistant to all available [Commercially available PIs at the time of trial enrollment.] PIs at baseline, excluding tipranavir and darunavir | 63% | 61%
Percentage of subjects with prior use of enfuvirtide | 20% | 17%
OBR=optimized background regimen

Week 96 outcomes for subjects on the recommended dose PREZISTA/ritonavir 600/100 mg twice daily from the pooled trials TMC114-C213 and TMC114-C202 are shown in Table 26.

Table 26: Outcomes of Randomized Treatment Through Week 96 of the Trials TMC114-C213 and TMC114-C202 (Pooled Analysis)
 | Randomized trials TMC114-C213 and TMC114-C202
 | PREZISTA/ritonavir 600/100 mg twice daily + OBR | Comparator PI(s) + OBR
 | N=131 | N=124
Virologic responders confirmed at least 1 log10HIV-1 RNA below baseline through Week 96 (<50 copies/mL at Week 96) | 57% (39%) | 10% (9%)
Virologic failures | 29% | 80%
Lack of initial response [Subjects who did not achieve at least a confirmed 0.5 log 10 HIV-1 RNA drop from baseline at Week 12.] | 8% | 53%
Rebounder [Subjects with an initial response (confirmed 1 log 10 drop in viral load), but without a confirmed 1 log 10 drop in viral load at Week 96.] | 17% | 19%
Never suppressed [Subjects who never reached a confirmed 1 log 10 drop in viral load before Week 96.] | 4% | 8%
Death or discontinuation due to adverse events | 9% | 3%
Discontinuation due to other reasons | 5% | 7%
OBR=optimized background regimen

In the pooled trials TMC114-C213 and TMC114-C202 through 48 weeks of treatment, the proportion of subjects with HIV-1 RNA less than 400 copies/mL in the arm receiving PREZISTA/ritonavir 600/100 mg twice daily compared to the comparator PI arm was 55.0% and 14.5%, respectively. In addition, the mean changes in plasma HIV-1 RNA from baseline were –1.69 log10copies/mL in the arm receiving PREZISTA/ritonavir 600/100 mg twice daily and –0.37 log10copies/mL for the comparator PI arm. The mean increase from baseline in CD4+ cell counts was higher in the arm receiving PREZISTA/ritonavir 600/100 mg twice daily (103 cells/mm^3) than in the comparator PI arm (17 cells/mm^3).

14.4 Pediatric Patients

The pharmacokinetic profile, safety and antiviral activity of PREZISTA/ritonavir were evaluated in 3 randomized, open-label, multicenter studies.

TMC114-C212

Treatment-experienced pediatric subjects between the ages of 6 and less than 18 years and weighing at least 20 kg were stratified according to their weight (greater than or equal to 20 kg to less than 30 kg, greater than or equal to 30 kg to less than 40 kg, greater than or equal to 40 kg) and received PREZISTA tablets with either ritonavir capsules or oral solution plus background therapy consisting of at least two non-protease inhibitor antiretroviral drugs. Eighty patients were randomized and received at least one dose of PREZISTA/ritonavir. Pediatric subjects who were at risk of discontinuing therapy due to intolerance of ritonavir oral solution (e.g., taste aversion) were allowed to switch to the capsule formulation. Of the 44 pediatric subjects taking ritonavir oral solution, 23 subjects switched to the 100 mg capsule formulation and exceeded the weight-based ritonavir dose without changes in observed safety.

The 80 randomized pediatric subjects had a median age of 14 (range 6 to less than 18 years), and were 71% male, 54% Caucasian, 30% Black, 9% Hispanic and 8% other. The mean baseline plasma HIV-1 RNA was 4.64 log10copies/mL, and the median baseline CD4+ cell count was 330 cells/mm^3(range: 6 to 1505 cells/mm^3). Overall, 38% of pediatric subjects had baseline plasma HIV-1 RNA ≥100,000 copies/mL. Most pediatric subjects (79%) had previous use of at least one NNRTI and 96% of pediatric subjects had previously used at least one PI.

Seventy-seven pediatric subjects (96%) completed the 24-week period. Of the patients who discontinued, one patient discontinued treatment due to an adverse event. An additional 2 patients discontinued for other reasons, one patient due to compliance and another patient due to relocation.

The proportion of pediatric subjects with HIV-1 RNA less than 400 copies/mL and less than 50 copies/mL was 64% and 50%, respectively. The mean increase in CD4+ cell count from baseline was 117 cells/mm^3.

TMC114-C228

Treatment-experienced pediatric subjects between the ages of 3 and less than 6 years and weighing greater than or equal to 10 kg to less than 20 kg received PREZISTA oral suspension with ritonavir oral solution plus background therapy consisting of at least two active non-protease inhibitor antiretroviral drugs. Twenty-one subjects received at least one dose of PREZISTA/ritonavir.

The 21 subjects had a median age of 4.4 years (range 3 to less than 6 years), and were 48% male, 57% Black, 29%, Caucasian and 14% other. The mean baseline plasma HIV-1 was 4.34 log10copies/mL, the median baseline CD4+ cell count was 927 × 10^6cells/L (range: 209 to 2,429 × 10^6cells/L) and the median baseline CD4+ percentage was 27.7% (range: 15.6% to 51.1%). Overall, 24% of subjects had a baseline plasma HIV-1 RNA greater than or equal to 100,000 copies/mL. All subjects had used greater than or equal to 2 NRTIs, 62% of subjects had used greater than or equal to 1 NNRTI and 76% had previously used at least one HIV PI.

Twenty subjects (95%) completed the 48 week period. One subject prematurely discontinued treatment due to vomiting assessed as related to ritonavir.

The proportion of subjects with HIV-1 RNA less than 50 copies/mL at Week 48 was 71%. The mean increase in CD4+ percentage from baseline was 4%. The mean change in CD4+ cell count from baseline was 187 × 10^6cells/L.

TMC114-C230

Treatment-naïve pediatric subjects between the ages of 12 and less than 18 years and weighing at least 40 kg received the adult recommended dose of PREZISTA/ritonavir 800/100 mg once daily plus background therapy consisting of at least two non-protease inhibitor antiretroviral drugs.

The 12 randomized pediatric subjects had a median age of 14.4 years (range 12.6 to 17.3 years), and were 33.3% male, 58.3% Caucasian and 41.7% Black. The mean baseline plasma HIV-1 RNA was 4.72 log10copies/mL, and the median baseline CD4+ cell count was 282 cells/mm^3(range: 204 to 515 cells/mm^3). Overall, 41.7% of pediatric subjects had baseline plasma HIV-1 RNA ≥100,000 copies/mL.

All subjects completed the 48 week treatment period.

The proportion of subjects with HIV-1 RNA less than 50 copies/mL and less than 400 copies/mL was 83.3% and 91.7%, respectively. The mean increase in CD4+ cell count from baseline was 221 × 10^6cells/L.

16 HOW SUPPLIED/STORAGE AND HANDLING

PREZISTA®(darunavir) 100 mg per mL oral suspension is a white to off-white opaque liquid supplied in amber-colored multiple-dose bottles containing 100 mg of darunavir per mL packaged with a 6 mL oral dosing syringe with 0.2 mL gradations.

PREZISTA®(darunavir) 75 mg tablets are supplied as white, caplet-shaped, film-coated tablets debossed with "75" on one side and "TMC" on the other side.

PREZISTA®(darunavir) 150 mg tablets are supplied as white, oval-shaped, film-coated tablets debossed with "150" on one side and "TMC" on the other side.

PREZISTA®(darunavir) 600 mg tablets are supplied as orange, oval-shaped, film-coated tablets debossed with "600MG" on one side and "TMC" on the other side.

PREZISTA®(darunavir) 800 mg tablets are supplied as dark red, oval-shaped, film-coated tablets debossed with "800" on one side and "T" on the other side.

PREZISTA is packaged in bottles in the following configuration:

- 100 mg/mL oral suspension – 200 mL bottles (NDC 59676-565-01)
- 75 mg tablets — bottles of 480 (NDC 59676-563-01)
- 150 mg tablets — bottles of 240 (NDC 59676-564-01)
- 600 mg tablets — bottles of 60 (NDC 59676-562-01)
- 800 mg tablets — bottles of 30 (NDC 59676-566-30)

Storage

PREZISTA Oral Suspension

- Store at 25°C (77°F); with excursions permitted to 15°–30°C (59°–86°F).
- Do not refrigerate or freeze. Avoid exposure to excessive heat.
- Store in the original container.
- Shake well before each usage.

PREZISTA Tablets

- Store at 25°C (77°F); with excursions permitted to 15°–30°C (59°–86°F).

Keep PREZISTA out of reach of children.

17 PATIENT COUNSELING INFORMATION

Advise the patient to read the FDA-approved patient labeling (Patient Information and Instruction for Use).

Instructions for Use

Advise patients to take PREZISTA and ritonavir with food every day on a regular dosing schedule, as missed doses can result in development of resistance. PREZISTA must always be used with ritonavir in combination with other antiretroviral drugs. Advise patients not to alter the dose of either PREZISTA or ritonavir, discontinue ritonavir, or discontinue therapy with PREZISTA without consulting their physician [see Dosage and Administration (2)] .

Hepatotoxicity

Inform patients that drug-induced hepatitis (e.g., acute hepatitis, cytolytic hepatitis) has been reported with PREZISTA co-administered with 100 mg of ritonavir. Advise patients about the signs and symptoms of liver problems [see Warnings and Precautions (5.2)] .

Severe Skin Reactions

Inform patients that skin reactions ranging from mild to severe, including Stevens-Johnson Syndrome, drug rash with eosinophilia and systemic symptoms, and toxic epidermal necrolysis, have been reported with PREZISTA co-administered with 100 mg of ritonavir. Advise patients to discontinue PREZISTA/ritonavir immediately if signs or symptoms of severe skin reactions develop. These can include but are not limited to severe rash or rash accompanied with fever, general malaise, fatigue, muscle or joint aches, blisters, oral lesions, conjunctivitis, hepatitis and/or eosinophilia [see Warnings and Precautions (5.3)] .

Drug Interactions

PREZISTA/ritonavir may interact with many drugs; therefore, advise patients to report to their healthcare provider the use of any other prescription or nonprescription medication or herbal products, including St. John's wort [see Contraindications (4), Warnings and Precautions (5.4, 5.5)and Drug Interactions (7)] .

Contraception

Instruct patients receiving combined hormonal contraception or the progestin only pill to use an effective alternative (non-hormonal) contraceptive method or add a barrier method during therapy with PREZISTA/ritonavir because hormonal levels may decrease [see Drug Interactions (7.3)and Use in Specific Populations (8.3)] .

Fat Redistribution

Inform patients that redistribution or accumulation of body fat may occur in patients receiving antiretroviral therapy, including PREZISTA/ritonavir, and that the cause and long-term health effects of these conditions are not known at this time [see Warnings and Precautions (5.7)] .

Immune Reconstitution Syndrome

Advise patients to inform their healthcare provider immediately of any symptoms of infection, as in some patients with advanced HIV infection (AIDS), signs and symptoms of inflammation from previous infections may occur soon after anti-HIV treatment is started [see Warnings and Precautions (5.8)].

Pregnancy Registry

Inform patients that there is an antiretroviral pregnancy registry to monitor fetal outcomes of pregnant women exposed to PREZISTA [see Use in Specific Populations (8.1)] .

Lactation

Instruct women with HIV-1 infection not to breastfeed because HIV-1 can be passed to the baby in breast milk [see Use in Specific Populations (8.2)] .

Manufactured for:
Janssen Products, LP
Horsham PA 19044, USA

PREZISTA®is a registered trademark of Janssen Pharmaceuticals.

© 2006 Janssen Pharmaceutical Companies

PATIENT INFORMATION

PREZISTA® (pre-ZIS-ta)
(darunavir)
oral suspension

PREZISTA® (pre-ZIS-ta)
(darunavir)
tablet

Read this Patient Information before you start taking PREZISTA and each time you get a refill. There may be new information. This information does not take the place of talking to your healthcare provider about your medical condition or your treatment.
Also read the Patient Information leaflet for ritonavir.

What is the most important information I should know about PREZISTA?

- Ask your healthcare provider or pharmacist about medicines that should not be taken with PREZISTA. For more information, see " Who should not take PREZISTA?" and " What should I tell my healthcare provider before taking PREZISTA?"
- PREZISTA may cause liver problems.Some people taking PREZISTA in combination with ritonavir have developed liver problems, which may be life-threatening. Your healthcare provider should do blood tests before and during your PREZISTA and ritonavir combination treatment. If you have chronic hepatitis B or C infection, your healthcare provider should check your blood tests more often because you have an increased chance of developing liver problems. Tell your healthcare provider if you have any of the below signs and symptoms of liver problems.

- dark (tea colored) urine
- yellowing of your skin or whites of your eyes
- pale colored stools (bowel movements)
- nausea

- vomiting
- pain or tenderness on your right side below your ribs
- loss of appetite
- tiredness

- PREZISTA may cause severe or life-threatening skin reactions or rash.Sometimes these skin reactions and skin rashes can become severe and require treatment in a hospital. Tell your healthcare provider right away if you develop a rash. Stoptaking PREZISTA and ritonavir combination treatment and tell your healthcare provider right away if you have any skin changes with symptoms below:

- fever
- tiredness
- muscle or joint pain

- blisters or skin lesions
- mouth sores or ulcers
- red or inflamed eyes, like "pink eye" (conjunctivitis)

Rash occurred more often in people taking PREZISTA and raltegravir together than with either drug separately, but was generally mild.
See " What are the possible side effects of PREZISTA?" for more information about side effects.

What is PREZISTA?
PREZISTA is a prescription HIV-1 (Human Immunodeficiency Virus-type 1) medicine used with ritonavir and other antiretroviral medicines to treat HIV-1 infection in adults and children 3 years of age and older. HIV is the virus that causes AIDS (Acquired Immune Deficiency Syndrome).
PREZISTA should not be used in children under 3 years of age.
When used with other antiretroviral medicines to treat HIV-1 infection, PREZISTA may help:

- reduce the amount of HIV-1 in your blood. This is called "viral load".
- increase the number of CD4+ (T) cells in your blood that help fight off other infections.

Reducing the amount of HIV-1 and increasing the CD4+ (T) cells in your blood may improve your immune system. This may reduce your risk of death or getting infections that can happen when your immune system is weak (opportunistic infections).
PREZISTA does not cure HIV-1 infection or AIDS.You must keep taking HIV-1 medicines to control HIV-1 infection and decrease HIV-related illnesses.
Avoid doing things that can spread HIV-1 infection to others:

- Do not share or re-use needles or other injection equipment.
- Do not share personal items that can have blood or body fluids on them, like toothbrushes and razor blades.
- Do not have any kind of sex without protection. Always practice safe sex by using a latex or polyurethane condom to lower the chance of sexual contact with semen, vaginal secretions, or blood.

Ask your healthcare provider if you have any questions on how to prevent passing HIV to other people.

Who should not take PREZISTA?
Do not take PREZISTA with any medicine that contains:

- alfuzosin
- colchicine, if you have liver or kidney problems
- dronedarone
- elbasvir and grazoprevir
- ergot-containing medicines:
  - dihydroergotamine
  - ergotamine tartrate
  - methylergonovine
- ivabradine
- lomitapide
- lovastatin
- lurasidone
- midazolam, when taken by mouth
- naloxegol
- pimozide
- ranolazine
- rifampin
- sildenafil, when used for the treatment of pulmonary arterial hypertension (PAH)
- simvastatin
- St. John's wort (Hypericum perforatum)
- triazolam

Serious problems can happen if you or your child take any of these medicines with PREZISTA. This is not a complete list of medicines. Therefore, tell your healthcare provider about allmedicines you take.

What should I tell my healthcare provider before taking PREZISTA?
Before taking PREZISTA, tell your healthcare provider if you:

- have liver problems, including hepatitis B or hepatitis C
- are allergic to sulfa medicines
- have high blood sugar (diabetes)
- have hemophilia
- have any other medical conditions
- are pregnant or plan to become pregnant. Tell your healthcare provider if you become pregnant while taking PREZISTA.
  - Pregnancy Registry: There is a pregnancy registry for women who take antiretroviral medicines during pregnancy. The purpose of this registry is to collect information about the health of you and your baby. Talk to your healthcare provider about how you can take part in this registry.
- are breastfeeding or plan to breastfeed. Do not breastfeed if you take PREZISTA.
  - You should not breastfeed if you have HIV-1 because of the risk of passing HIV-1 to your baby.
  - It is not known if PREZISTA can pass into your breast milk.
  - Talk to your healthcare provider about the best way to feed your baby.

Tell your healthcare provider about all the medicines you take,including prescription and over-the-counter medicines, topical creams, vitamins, and herbal supplements. Some medicines interact with PREZISTA. Keep a list of your medicines to show your healthcare provider and pharmacist.

- You can ask your healthcare provider or pharmacist for a list of medicines that interact with PREZISTA.
- Do not start taking a new medicine without telling your healthcare provider.Your healthcare provider can tell you if it is safe to take PREZISTA with other medicines.

How should I take PREZISTA?

- Take PREZISTA exactly as your healthcare provider tells you.
- You must take ritonavir at the same time as PREZISTA.
- Do not change your dose or stop treatment with PREZISTA without talking to your healthcare provider.
- Take PREZISTA and ritonavir with food.
- If you have difficulty swallowing PREZISTA tablets, PREZISTA oral suspension is also available. Your healthcare provider will help decide whether PREZISTA tablets or oral suspension is right for you.
- If your child is taking PREZISTA, your child's healthcare provider will decide the right dose based on your child's weight. Your child's healthcare provider will tell you how much PREZISTA (tablets or oral suspension) and how much ritonavir (capsules, tablets or solution) your child should take. Your child should take PREZISTA with ritonavir with food. If your child does not tolerate ritonavir oral solution, ask your child's healthcare provider for advice.
- PREZISTA oral suspension should be given with the supplied oral dosing syringe. Shake the suspension well before each use. See the " Instructions for Use" that come with PREZISTA oral suspension for information about the right way to prepare and take a dose.
- It is important that you do not miss or skip doses of PREZISTA during treatment.
- If you take too much PREZISTA, call your healthcare provider or go to the nearest hospital emergency room right away.

What are the possible side effects of PREZISTA?
PREZISTA may cause serious side effects, including:

- See " What is the most important information I should know about PREZISTA?"
- Diabetes and high blood sugar (hyperglycemia).Some people who take protease inhibitors including PREZISTA can get high blood sugar, develop diabetes, or your diabetes can get worse. Tell your healthcare provider if you notice an increase in thirst or urinate often while taking PREZISTA.
- Changes in body fatcan happen in people who take HIV-1 medicines. The changes may include an increased amount of fat in the upper back and neck ("buffalo hump"), breast, and around the middle of your body (trunk). Loss of fat from the legs, arms, and face may also happen. The exact cause and long-term health effects of these conditions are not known.
- Changes in your immune system (Immune Reconstitution Syndrome)can happen when you start taking HIV-1 medicines. Your immune system may get stronger and begin to fight infections that have been hidden in your body for a long time. Tell your healthcare provider right away if you start having new symptoms after starting your HIV-1 medicine.
- Increased bleeding for hemophiliacs.Some people with hemophilia have increased bleeding with protease inhibitors including PREZISTA.

The most common side effects of PREZISTA include:

- diarrhea
- nausea
- rash

- headache
- stomach-area (abdominal) pain
- vomiting

Tell your healthcare provider if you have any side effect that bothers you or that does not go away.
These are not all of the possible side effects of PREZISTA.
Call your doctor for medical advice about side effects. You may report side effects to FDA at 1-800-FDA-1088.

How should I store PREZISTA?

- Store PREZISTA oral suspension and tablets at room temperature 77°F (25°C).
- Do not refrigerate or freeze PREZISTA oral suspension.
- Keep PREZISTA oral suspension away from high heat.
- PREZISTA oral suspension should be stored in the original container.

Keep PREZISTA and all medicines out of the reach of children.

General information about the safe and effective use of PREZISTA.
Medicines are sometimes prescribed for purposes other than those listed in a Patient Information leaflet. Do not use PREZISTA for a condition for which it was not prescribed. Do not give PREZISTA to other people even if they have the same condition you have. It may harm them.
This leaflet summarizes the most important information about PREZISTA. If you would like more information, talk to your healthcare provider. You can ask your healthcare provider or pharmacist for information about PREZISTA that is written for health professionals. For more information, call 1-800-526-7736.

What are the ingredients in PREZISTA?
Active ingredient: darunavir
Inactive ingredients:
PREZISTA oral suspension:citric acid monohydrate, hydrochloric acid (for pH adjustment), hydroxypropyl cellulose, masking flavor, methylparaben sodium, microcrystalline cellulose, purified water, sodium carboxymethylcellulose, strawberry cream flavor, and sucralose.
PREZISTA 75 mg and 150 mg tablets:colloidal silicon dioxide, crospovidone, magnesium stearate, microcrystalline cellulose. The film coating contains: OPADRY®White (polyethylene glycol 3350, polyvinyl alcohol-partially hydrolyzed, talc, titanium dioxide).
PREZISTA 600 mg tablets:colloidal silicon dioxide, crospovidone, magnesium stearate, microcrystalline cellulose. The film coating contains: OPADRY®Orange (FD&C Yellow No. 6, polyethylene glycol 3350, polyvinyl alcohol-partially hydrolyzed, talc, titanium dioxide).
PREZISTA 800 mg tablets:colloidal silicon dioxide, crospovidone, magnesium stearate, microcrystalline cellulose, hypromellose. The film coating contains: OPADRY®Dark Red (iron oxide red, polyethylene glycol 3350, polyvinyl alcohol-partially hydrolyzed, talc, titanium dioxide).
Manufactured for: Janssen Products, LP, Horsham PA 19044, USA
PREZISTA®is a registered trademark of Janssen Pharmaceuticals
© 2006 Janssen Pharmaceutical Companies

This Patient Information has been approved by the U.S. Food and Drug Administration.

Revised: 03/2023

INSTRUCTIONS FOR USE PREZISTA (pre-ZIS-ta) (darunavir) oral suspension

Be sure that you read, understand, and follow these Instructions for Use so that you measure and take PREZISTA oral suspension correctly. Ask your healthcare provider if you are not sure.

Each PREZISTA oral suspension carton contains:

- 1 bottle of PREZISTA oral suspension
- Oral dosing syringe
- 1 oral syringe adapter

Important information for use:

- Shake PREZISTA oral suspension well before each use.
- PREZISTA oral suspension should be given with the oral dosing syringe provided to make sure you measure the right amount. The oral dosing syringe provided with your PREZISTA oral suspension should not be used for any other medicines.

- Shake the bottle.
  - Shake the bottle well before each use (See Figure A).

Figure A: Shake the bottle

- Open the bottle of PREZISTA oral suspension.
  - Open the bottle by pushing downward on the cap and twisting it in the direction of the arrow (counter-clockwise) (See Figure B).

Figure B: Opening the bottle

- The first time a bottle of PREZISTA oral suspension is used:
  - Insert the oral syringe adapter into the bottle. Press on the adapter until it is even with the top of the bottle (See Figure C).
  - Do notremove the oral syringe adapter from the bottle once inserted.

Figure C: Inserting the adapter

- Insert the oral dosing syringe.
  - Fully push down (depress) the plunger of the syringe.
  - Insert the syringe into the opening of the oral syringe adapter until it is firmly in place (See Figure D).

Figure D: Inserting the syringe

- Withdraw the prescribed amount of PREZISTA oral suspension.
  - Turn the bottle upside down. Gently pull back the plunger of the syringe until the bottom of the plunger is even with the markings on the syringe for the prescribed dose (See Figure E). If you see air bubbles in the syringe, push the plunger in to empty the oral suspension back into the bottle. Then repeat steps 4 and 5.
  - If you or your child's dose of PREZISTA oral suspension is more than 6 mL, you will need to divide the dose. Follow the instructions given to you by your healthcare provider or pharmacist about how to divide the dose.

Figure E: Withdrawing the Oral Suspension

- Turn the bottle upright and remove the syringe from the bottle by pulling straight up on the oral dosing syringe (See Figure F).

Figure F: Removing the syringe

- Take the dose of PREZISTA.
  - Place the tip of the oral dosing syringe in the mouth.
  - Press on the plunger of the syringe towards the mouth (See Figure G).

If you or your child's dose is more than 6 mL you will need to divide the dose. Follow the instructions given to you by your healthcare provider or pharmacist about how to divide the dose, and repeat steps 4 through 7.

Figure G: Taking the dose of PREZISTA

- Close the bottle with the cap after use.
  - Close the bottle by twisting the cap in the direction of the arrow (clockwise) (See Figure H).

Figure H: Closing the bottle

- Remove the plunger from the barrel by pulling the plunger and barrel away from each other (See Figure I). Rinse both parts of the syringe with water and allow to air dry after each use.

Figure I: Removing the plunger from the barrel

- After air drying, put the oral dosing syringe back together by inserting the plunger into the barrel (See Figure J). Store the oral dosing syringe with PREZISTA oral suspension.

Figure J: Putting the syringe back together

How should I store PREZISTA?

- Store PREZISTA oral suspension and the oral dosing syringe at room temperature 77°F (25°C).
- Do not refrigerate or freeze PREZISTA oral suspension.
- Keep PREZISTA oral suspension away from high heat.
- Store PREZISTA oral suspension in the original container.

Keep PREZISTA and all medicines out of the reach of children.

This Instruction for Use has been approved by the U.S. Food and Drug Administration.

Manufactured for:
Janssen Products, LP, Horsham PA 19044

Revised: May 2022
©2006 Janssen Pharmaceutical Companies

PRINCIPAL DISPLAY PANEL - 75 mg Tablet Bottle Label

NDC 59676- 563-01

PREZISTA®
(darunavir) tablets

75 mg

ALERT
Find out about medicines that
should NOT be taken with PREZISTA

Rx only

480 Tablets

Johnson

&Johnson

PRINCIPAL DISPLAY PANEL - 150 mg Tablet Bottle Label

NDC 59676- 564-01

PREZISTA®
(darunavir) tablets

150 mg

ALERT
Find out about medicines that
should NOT be taken with PREZISTA.

Rx only

240 Tablets

Johnson

&Johnson

PRINCIPAL DISPLAY PANEL - 600 mg Tablet Bottle Label

NDC 59676- 562-01

PREZISTA®
(darunavir) tablets

600 mg

ALERT
Find out about medicines that
should NOT be taken with PREZISTA.

Rx only

60 Tablets

Johnson

&Johnson

PRINCIPAL DISPLAY PANEL - 800 mg Tablet Bottle Label

NDC 59676- 566-30

PREZISTA®
(darunavir) tablets

800 mg

ALERT
Find out about medicines that
should NOT be taken with PREZISTA.

Rx only

30 Tablets

Johnson

&Johnson

PRINCIPAL DISPLAY PANEL - 200 mL Bottle Carton

NDC 59676- 565-01

PREZISTA®
(darunavir) Oral Suspension

100 mg per mL

DISPENSING:For information concerning

proper usage of the oral dosing syringe,
see accompanying PATIENT INFORMATION

and INSTRUCTIONS FOR USE.

ALERT

Find out about medicines

that should NOT be taken

with PREZISTA.

Rx only

200 mL

Johnson

&Johnson